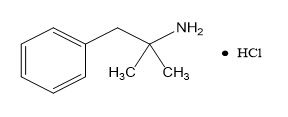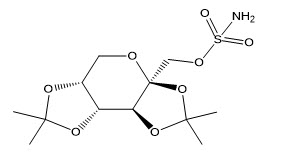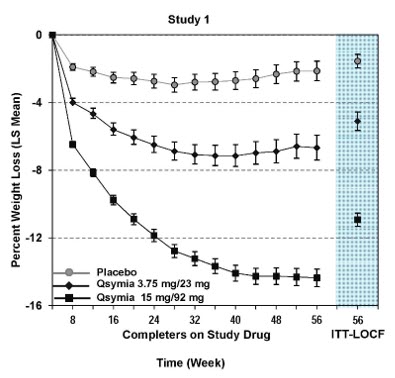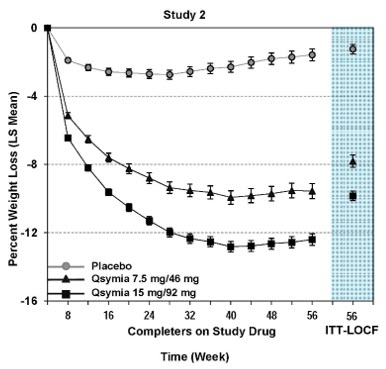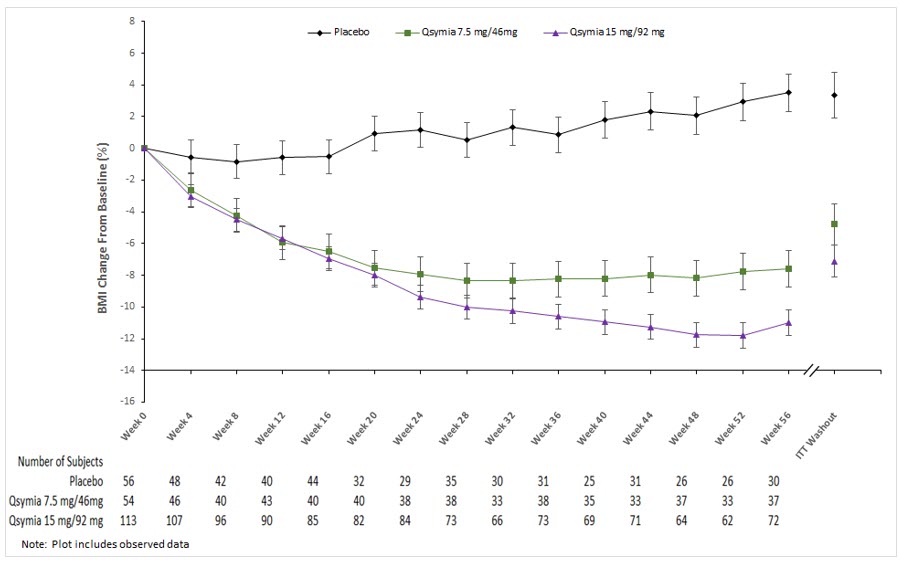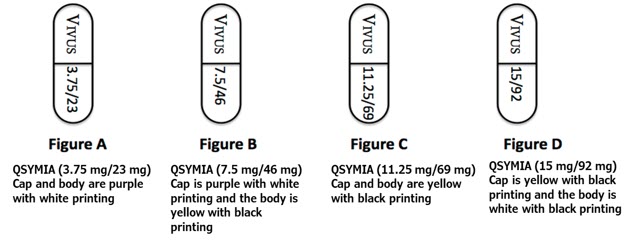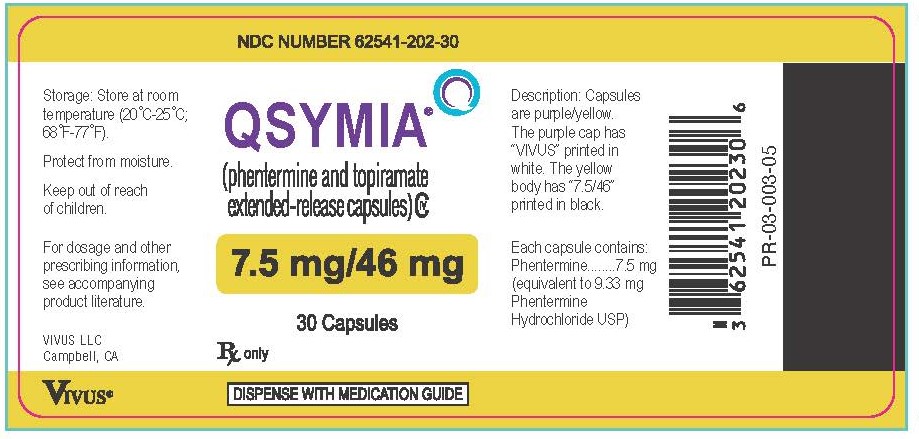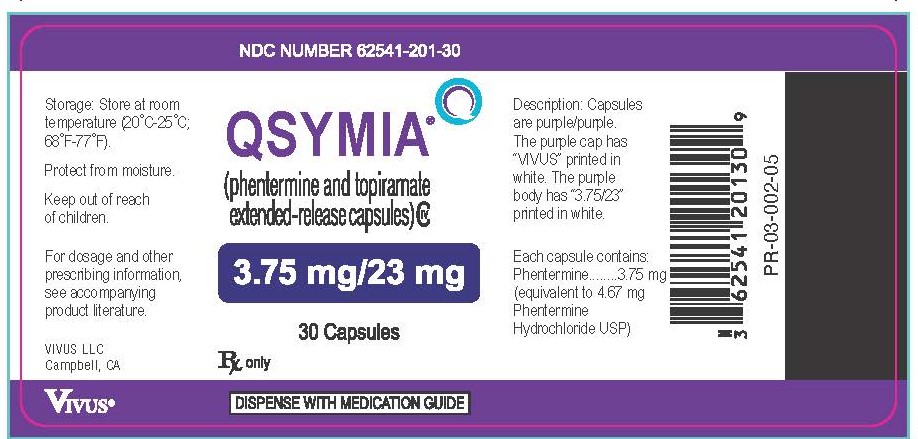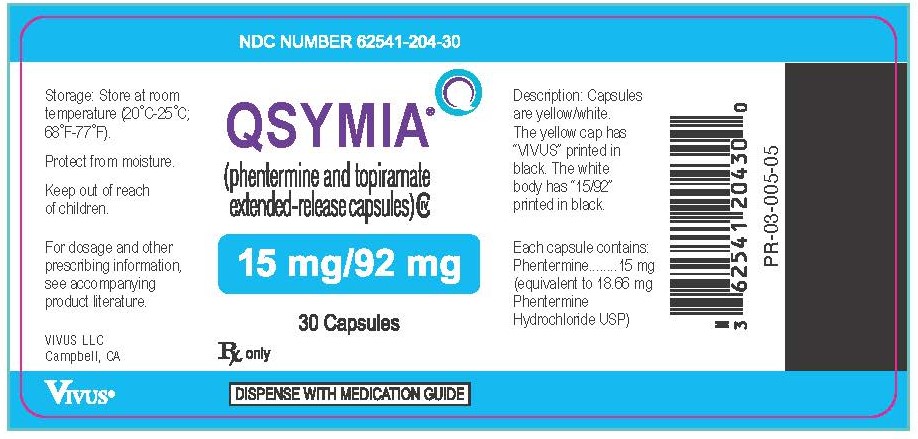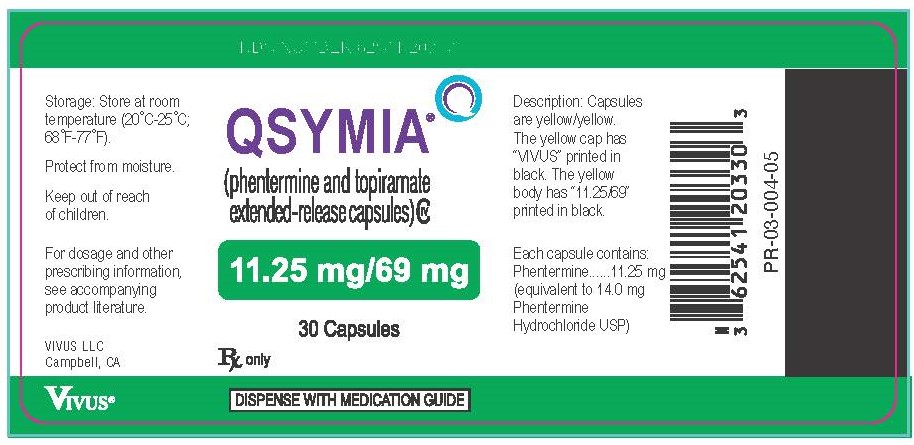 DRUG LABEL: Qsymia
NDC: 62541-202 | Form: CAPSULE, EXTENDED RELEASE
Manufacturer: Vivus LLC
Category: prescription | Type: HUMAN PRESCRIPTION DRUG LABEL
Date: 20250908
DEA Schedule: CIV

ACTIVE INGREDIENTS: PHENTERMINE HYDROCHLORIDE 7.5 mg/1 1; TOPIRAMATE 46 mg/1 1
INACTIVE INGREDIENTS: MICROCRYSTALLINE CELLULOSE; ETHYLCELLULOSE, UNSPECIFIED; POVIDONE K30; GELATIN, UNSPECIFIED; TALC; TITANIUM DIOXIDE; FD&C BLUE NO. 1; FD&C RED NO. 3; FD&C YELLOW NO. 5; FD&C YELLOW NO. 6; SUCROSE; STARCH, CORN

HIGHLIGHTS OF PRESCRIBING INFORMATION

These highlights do not include all the information needed to use QSYMIA®safely and effectively. See full prescribing information for QSYMIA.
QSYMIA (phentermine and topiramate extended-release capsules), for oral use, CIV
Initial U.S. Approval: 2012

1 INDICATIONS AND USAGE

QSYMIA is a combination of phentermine, a sympathomimetic amine anorectic, and topiramate, indicated in combination with a reduced-calorie diet and increased physical activity to reduce excess body weight and maintain weight reduction long term in:

- Adults and pediatric patients aged 12 years and older with obesity (1)
- Adults with overweight in the presence of at least one weight-related comorbid condition (1)

Limitations of Use:

- The effect of QSYMIA on cardiovascular morbidity and mortality has not been established (1).
- The safety and effectiveness of QSYMIA in combination with other products intended for weight loss, including prescription and over-the-counter drugs, and herbal preparations, have not been established (1).

2 DOSAGE AND ADMINISTRATION

- Take orally once daily in morning. Avoid administration in evening to prevent insomnia (2.2).
- Recommended starting dosage is 3.75 mg/23 mg (phentermine mg/topiramate mg) daily for 14 days; then increase to 7.5 mg/46 mg daily (2.2).
- Escalate dosage based on weight loss in adults or BMI reduction in pediatric patients. See the Full Prescribing Information for details regarding discontinuation or dosage escalation (2.2).
- Gradually discontinue 15 mg/92 mg dosage to prevent possible seizure (2.3).
- Do not exceed 7.5 mg/46 mg dosage for patients with moderate or severe renal impairment or patients with moderate hepatic impairment (2.4, 2.5).

3 DOSAGE FORMS AND STRENGTHS

Extended-release capsules: (phentermine mg/topiramate mg)

- 3.75 mg/23 mg (3)
- 7.5 mg/46 mg (3)
- 11.25 mg/69 mg (3)
- 15 mg/92 mg (3)

4 CONTRAINDICATIONS

- Pregnancy (4)
- Glaucoma (4)
- Hyperthyroidism (4)
- Taking or within 14 days of stopping monoamine oxidase inhibitors (4)
- Known hypersensitivity to any component of QSYMIA or idiosyncrasy to sympathomimetic amines (4)

5 WARNINGS AND PRECAUTIONS

- Embryo-Fetal Toxicity: Can cause fetal harm. In patients who can become pregnant, a negative pregnancy test is recommended before initiating QSYMIA and monthly during therapy; advise use of effective contraception. QSYMIA is available through a limited program under a Risk Evaluation and Mitigation Strategy (REMS) (5.1).
- Suicidal Behavior and Ideation: Monitor for depression or suicidal thoughts. Discontinue QSYMIA if symptoms develop (5.2).
- Risk of Ophthalmologic Adverse Reactions: Acute myopia and secondary angle closure glaucoma have been reported. Immediately discontinue QSYMIA if symptoms develop. Consider QSYMIA discontinuation if visual field defects occur (5.3).
- Mood and Sleep Disorders: Consider dosage reduction or discontinuation for clinically significant or persistent mood or sleep disorder symptoms (5.4).
- Cognitive Impairment: May cause disturbances in attention or memory, or speech/language problems. Caution patients about operating automobiles or hazardous machinery when starting treatment (5.5).
- Slowing of Linear Growth: Consider dosage reduction or discontinuation if pediatric patients are not growing or gaining height as expected (5.6).
- Metabolic Acidosis: Measure electrolytes before and during treatment. If persistent metabolic acidosis develops, reduce dosage or discontinue QSYMIA (5.7).
- Decrease in Renal Function: Measure creatinine before and during treatment. For persistent creatinine elevations, reduce dosage or discontinue QSYMIA (5.8).
- Serious Skin Reactions:QSYMIA should be discontinued at the first sign of a rash, unless the rash is clearly not drug-related (5.13).

6 ADVERSE REACTIONS

Most common adverse reactions in:

- Adults (incidence ≥ 5% and at least 1.5 times placebo) are: paraesthesia, dizziness, dysgeusia, insomnia, constipation, and dry mouth (6.1).
- Pediatric patients aged 12 years and older (incidence ≥4% and greater than placebo) are: depression, dizziness, arthralgia, pyrexia, influenza, and ligament sprain (6.1).

To report SUSPECTED ADVERSE REACTIONS, contact VIVUS LLC, at 1-888-998-4887 or FDA at 1-800-FDA-1088 or www.fda.gov/medwatch.

7 DRUG INTERACTIONS

- Oral Contraceptives: Altered exposure of progestin and estrogen may cause irregular bleeding, but not increased risk of pregnancy. Advise patients not to discontinue oral contraceptives if spotting occurs (7).
- CNS Depressants Including Alcohol: May potentiate CNS depressant effects. Avoid excessive use of alcohol (7).
- Non-potassium Sparing Diuretics: May potentiate hypokalemia. Measure potassium before and during treatment (7).

8 USE IN SPECIFIC POPULATIONS

- Lactation: Breastfeeding not recommended (8.2).

FULL PRESCRIBING INFORMATION

1 INDICATIONS AND USAGE

QSYMIA is indicated in combination with a reduced-calorie diet and increased physical activity to reduce excess body weight and maintain weight reduction long term in:

- Adults and pediatric patients aged 12 years and older with obesity
- Adults with overweight in the presence of at least one weight-related comorbid condition

Limitations of Use

- The effect of QSYMIA on cardiovascular morbidity and mortality has not been established.
- The safety and effectiveness of QSYMIA in combination with other products intended for weight loss, including prescription drugs, over-the-counter drugs, and herbal preparations, have not been established.

2 DOSAGE AND ADMINISTRATION

2.1 Recommended Testing Prior to and During Treatment with QSYMIA

Prior to QSYMIA initiation and during treatment with QSYMIA, the following is recommended:

- Obtain a negative pregnancy test before initiating QSYMIA in patients who can become pregnant and monthly during QSYMIA therapy. QSYMIA is contraindicated during pregnancy [see Contraindications (4), Warnings and Precautions (5.1), and Use in Specific Populations (8.3)] .
- Obtain a blood chemistry profile that includes bicarbonate, creatinine, and potassium in all patients, and glucose in patients with type 2 diabetes mellitus on antidiabetic medication prior to initiating QSYMIA treatment and periodically during treatment [see Warnings and Precautions (5.7, 5.8, 5.12)] .

2.2 Recommended Dosage and Administration

The recommended dosage, titration, and administration of QSYMIA are as follows:

- Take QSYMIA orally once daily in the morning with or without food. Avoid administration of QSYMIA in the evening due to the possibility of insomnia.
- The recommended starting dosage of QSYMIA is one capsule (containing 3.75 mg of phentermine and 23 mg of topiramate) (3.75 mg/23 mg) taken orally once daily for 14 days; after 14 days increase to the recommended dosage of QSYMIA 7.5 mg/46 mg orally once daily.
- After 12 weeks of treatment with QSYMIA 7.5 mg/46 mg, evaluate weight loss for adults or BMI reduction for pediatric patients aged 12 years and older. If an adult patient has not lost at least 3% of baseline body weight or a pediatric patient has not experienced a reduction of at least 3% of baseline BMI, increase the dosage to QSYMIA 11.25 mg/69 mg orally once daily for 14 days; followed by an increase in the dosage to QSYMIA 15 mg/92 mg orally once daily.
- After 12 weeks of treatment with QSYMIA 15 mg/92 mg, evaluate weight loss for adults or BMI reduction for pediatric patients aged 12 years and older. If an adult patient has not lost at least 5% of baseline body weight or a pediatric patient has not experienced a reduction of at least 5% of baseline BMI, discontinue QSYMIA [see Dosage and Administration (2.3)] , as it is unlikely that the patient will achieve and sustain clinically meaningful weight loss with continued treatment.
- Monitor the rate of weight loss in pediatric patients. If weight loss exceeds 2 lbs (0.9 kg)/week, consider dosage reduction.

2.3 Discontinuation of QSYMIA 15 mg/92 mg

Discontinue QSYMIA 15 mg/92 mg gradually by taking QSYMIA 15 mg/92 mg orally once daily every other day for at least 1 week prior to stopping treatment altogether, due to the possibility of precipitating a seizure [see Warnings and Precautions (5.9) and Drug Abuse and Dependence (9.3)] .

2.4 Recommended Dosage in Patients with Renal Impairment

- The recommended dosage in patients with mild (CrCl greater or equal to 50 and less than 80 mL/min) renal impairment is the same as the recommended dosage for patients with normal renal function [see Warnings and Precautions (5.9), Use in Specific Populations (8.6), and Clinical Pharmacology (12.3)] .
- In patients with severe [creatinine clearance (CrCl) less than 30 mL/min] or moderate (CrCl greater than or equal to 30 and less than 50 mL/min) renal impairment (CrCl calculated using the Cockcroft-Gault equation with actual body weight), the maximum recommended dosage is QSYMIA 7.5 mg/46 mg once daily.
- Avoid use of QSYMIA in patients with end-stage renal disease on dialysis.

2.5 Recommended Dosage in Patients with Hepatic Impairment

- The recommended dosage of QSYMIA in patients with mild hepatic impairment (Child-Pugh 5 - 6) is the same as the recommended dosage in patients with normal hepatic function [see Use in Specific Populations (8.7) and Clinical Pharmacology (12.3)] .
- In patients with moderate hepatic impairment (Child-Pugh score 7 - 9), the maximum recommended dosage is QSYMIA 7.5 mg/46 mg orally once daily.
- Avoid use of QSYMIA in patients with severe hepatic impairment (Child-Pugh score 10 - 15).

3 DOSAGE FORMS AND STRENGTHS

QSYMIA extended-release capsules are available in four strengths (phentermine mg/topiramate mg):

- 3.75 mg/23 mg - purple cap imprinted with VIVUS and purple body imprinted with 3.75/23
- 7.5 mg/46 mg - purple cap imprinted with VIVUS and yellow body imprinted with 7.5/46
- 11.25 mg/69 mg - yellow cap imprinted with VIVUS and yellow body imprinted with 11.25/69
- 15 mg/92 mg - yellow cap imprinted with VIVUS and white body imprinted with 15/92

4 CONTRAINDICATIONS

QSYMIA is contraindicated in patients:

- Who are pregnant [see Warnings and Precautions (5.1)and Use in Specific Populations (8.1)]
- With glaucoma [see Warnings and Precautions (5.3)]
- With hyperthyroidism
- Taking or within 14 days of stopping a monoamine oxidase inhibitors [see Drug Interactions (7)]
- With known hypersensitivity to phentermine, topiramate or any of the excipients in QSYMIA, or idiosyncrasy to the sympathomimetic amines [see Adverse Reactions (6.2)] .

5 WARNINGS AND PRECAUTIONS

5.1 Embryo-Fetal Toxicity

QSYMIA can cause fetal harm. Data from pregnancy registries and epidemiologic studies indicate that a fetus exposed to topiramate in the first trimester of pregnancy has an increased risk of major congenital malformations, including but not limited to cleft lip and/or cleft palate (oral clefts), and of being small for gestational age (SGA). When multiple species of pregnant animals received topiramate at clinically relevant doses, structural malformations, including craniofacial defects, and reduced fetal weights occurred in offspring. A negative pregnancy test is recommended before initiating QSYMIA treatment in patients who can become pregnant and monthly during QSYMIA therapy. Advise patients who can become pregnant of the potential risk to a fetus and to use effective contraception during QSYMIA therapy [see Use in Specific Populations (8.1, 8.3)] .

QSYMIA Risk Evaluation and Mitigation Strategy (REMS)

Because of the teratogenic risk associated with QSYMIA therapy, QSYMIA is available through a limited program under the REMS. Under the QSYMIA REMS, only certified pharmacies may distribute QSYMIA. Further information is available at www.QSYMIAREMS.com or by telephone at 1-888-998-4887.

5.2 Suicidal Behavior and Ideation

Antiepileptic drugs (AEDs), including topiramate, increase the risk of suicidal thoughts or behavior in patients taking these drugs for any indication. Pooled analyses of 199 placebo-controlled clinical studies (monotherapy and adjunctive therapy, median treatment duration 12 weeks) of 11 different AEDs across several indications showed that patients randomized to one of the AEDs had approximately twice the risk (adjusted Relative Risk 1.8, 95% CI 1.2, 2.7) of suicidal thinking or behavior compared to patients randomized to placebo. The estimated incidence rate of suicidal behavior or ideation among 27,863 AED-treated patients was 0.43%, compared to 0.24% among 16,029 placebo-treated patients, representing an increase of approximately one case of suicidal thinking or behavior for every 530 patients treated. There were four suicides in AED-treated patients in the trials and none in placebo-treated patients, but the number is too small to allow any conclusion about AED effect on suicide. The increased risk of suicidal thoughts or behavior with AEDs was observed as early as 1 week after starting drug treatment with AEDs and persisted for the duration of treatment assessed. Because most trials included in the analysis did not extend beyond 24 weeks, the risk of suicidal thoughts or behavior beyond 24 weeks could not be assessed. The risk of suicidal thoughts or behavior was generally consistent among drugs in the data analyzed. The finding of increased risk with AEDs of varying mechanisms of action and across a range of indications suggests that the risk applies to all AEDs used for any indication. The risk did not vary substantially by age in the clinical trials analyzed.

In a QSYMIA clinical trial of pediatric patients aged 12 years and older, 1 (0.6%) of the 167 QSYMIA-treated patients reported suicidal ideation and behavior which required hospitalization. No placebo-treated patients reported suicidal behavior or ideation.

Monitor all patients for the emergence or worsening of depression, suicidal thoughts or behavior, and/or any unusual changes in mood or behavior. Discontinue QSYMIA in patients who experience suicidal thoughts or behaviors [see Warnings and Precautions (5.9)] . Avoid QSYMIA in patients with a history of suicidal attempts or active suicidal ideation.

5.3 Risk of Ophthalmologic Adverse Reactions

Acute Myopia and Secondary Angle Closure Glaucoma

A syndrome consisting of acute myopia associated with secondary angle closure glaucoma has been reported in patients treated with topiramate. Symptoms include acute onset of decreased visual acuity and/or ocular pain. Ophthalmologic findings can include myopia, mydriasis, anterior chamber shallowing, ocular hyperemia (redness), choroidal detachments, retinal pigment epithelial detachments, macular striae, and increased intraocular pressure. This syndrome may be associated with supraciliary effusion resulting in anterior displacement of the lens and iris, with secondary angle closure glaucoma. Symptoms typically occur within 1 month of initiating treatment with topiramate but may occur at any time during therapy. In contrast to primary narrow angle glaucoma, which is rare under 40 years of age, secondary angle closure glaucoma associated with topiramate has been reported in pediatric patients as well as adults. The primary treatment to reverse symptoms is discontinuation of QSYMIA as rapidly as possible in consultation with the treating physician. Elevated intraocular pressure of any etiology, if left untreated, can lead to serious sequelae including permanent loss of vision.

Visual Field Defects

Visual field defects (independent of elevated intraocular pressure) have been reported in clinical trials and in postmarketing experience in patients receiving topiramate. In clinical trials, most of these events were reversible after topiramate discontinuation. If visual problems occur at any time during treatment, consider discontinuing QSYMIA.

5.4 Mood and Sleep Disorders

QSYMIA can cause mood disorders, including depression and anxiety, as well as insomnia. Patients with a history of depression may be at increased risk of recurrent depression or other mood disorders while taking QSYMIA [see Adverse Reactions (6.1)] .

Consider dosage reduction or discontinuation of QSYMIA if clinically significant or persistent symptoms occur. Discontinue QSYMIA if patients have symptoms of suicidal ideation or behavior [see Warnings and Precautions (5.2)] .

5.5 Cognitive Impairment

QSYMIA can cause cognitive dysfunction (e.g., impairment of concentration/attention, difficulty with memory, and speech or language problems, particularly word-finding difficulties). Rapid titration or high initial doses of QSYMIA may be associated with higher rates of cognitive events such as attention, memory, and language/word-finding difficulties [see Adverse Reactions (6.1)] . The concomitant use of alcohol or central nervous system (CNS) depressant drugs with QSYMIA may potentiate CNS depression or other centrally mediated effects of these agents, such as dizziness, cognitive adverse reactions, drowsiness, light-headedness, impaired coordination, and somnolence.

Caution patients about operating hazardous machinery, including automobiles, until they are reasonably certain QSYMIA therapy does not affect them adversely. Caution patients against excessive alcohol intake while receiving QSYMIA.

If cognitive dysfunction persists, consider dosage reduction or discontinuation of QSYMIA [see Warnings and Precautions (5.9)] .

5.6 Slowing of Linear Growth

QSYMIA is associated with a reduction in height velocity (centimeters of height gained per year) in obese pediatric patients 12 to 17 years of age. In a 56-week study, average height increased from baseline in both QSYMIA- and placebo-treated patients; however, a lower height velocity of -1.3 to -1.4 cm/year was observed in QSYMIA-treated compared to placebo-treated patients. Monitor height velocity in pediatric patients treated with QSYMIA. Consider dosage reduction or discontinuation of QSYMIA if pediatric patients are not growing or gaining height as expected [see Warnings and Precautions (5.9)] .

5.7 Metabolic Acidosis

Hyperchloremic, non-anion gap, metabolic acidosis (decreased serum bicarbonate below the normal reference range in the absence of chronic respiratory alkalosis) has been reported in patients treated with QSYMIA [see Adverse Reactions (6.1)] . Manifestations of acute or chronic metabolic acidosis may include hyperventilation, nonspecific symptoms such as fatigue and anorexia, or more severe sequelae including cardiac arrhythmias or stupor. Chronic, untreated metabolic acidosis may increase the risk for nephrolithiasis or nephrocalcinosis and may also result in osteomalacia (referred to as rickets in pediatric patients) and/or osteoporosis with an increased risk for fractures. Chronic metabolic acidosis in pediatric patients may also reduce growth rates, which may decrease the maximal height achieved.

Conditions or therapies that predispose to acidosis (i.e., renal disease, severe respiratory disorders, status epilepticus, diarrhea, surgery, or ketogenic diet) may be additive to the bicarbonate lowering effects of QSYMIA. Concomitant use of QSYMIA and a carbonic anhydrase inhibitor may increase the severity of metabolic acidosis and may also increase the risk of kidney stone formation [see Warnings and Precautions (5.10)] . Avoid use of QSYMIA with other carbonic anhydrase inhibitors. If concomitant use of QSYMIA with another carbonic anhydrase inhibitor is unavoidable, the patient should be monitored for the appearance or worsening of metabolic acidosis.

Measure electrolytes including serum bicarbonate prior to starting QSYMIA and during QSYMIA treatment. In QSYMIA clinical trials, the peak reduction in serum bicarbonate typically occurred within 4 weeks of titration to the assigned dose, and in most patients, there was a correction of bicarbonate by week 56, without any dosage reduction. However, if persistent metabolic acidosis develops while taking QSYMIA, reduce the dosage or discontinue QSYMIA [see Warnings and Precautions (5.9)] .

5.8 Decrease in Renal Function

QSYMIA can cause an increase in serum creatinine that reflects a decrease in renal function (glomerular filtration rate). In clinical trials, peak increases in serum creatinine were observed after 4 to 8 weeks of treatment. On average, serum creatinine gradually declined but remained elevated over baseline creatinine values. The changes in serum creatinine (and measured GFR) with short-term (4-weeks) QSYMIA treatment appear reversible with treatment discontinuation, but the effect of chronic treatment on renal function is not known.

Measure serum creatinine prior to starting QSYMIA and during QSYMIA treatment. If persistent elevations in creatinine occur, reduce the dosage or discontinue QSYMIA [see Warnings and Precautions (5.9), Adverse Reactions (6.1), and Clinical Pharmacology (12.2)] .

5.9 Risk of Seizures with Abrupt Withdrawal of QSYMIA

Abrupt withdrawal of topiramate has been associated with seizures in individuals without a history of seizures or epilepsy. In situations where immediate termination of QSYMIA is medically required, appropriate monitoring is recommended. Patients discontinuing QSYMIA 15 mg/92 mg should be gradually tapered to reduce the possibility of precipitating a seizure [see Dosage and Administration (2.3) and Drug Abuse and Dependence (9.3)] .

5.10 Kidney Stones

QSYMIA has been associated with kidney stone formation [see Adverse Reactions (6.1)] . Topiramate inhibits carbonic anhydrase activity and promotes kidney stone formation by reducing urinary citrate excretion and increasing urine pH. Patients on a ketogenic diet may be at increased risk for kidney stone formation. An increase in urinary calcium and a marked decrease in urinary citrate was observed in topiramate-treated pediatric patients in a one-year, active-controlled study. Increased ratio of urinary calcium/citrate increases the risk of kidney stones and/or nephrocalcinosis.

Avoid the use of QSYMIA with other drugs that inhibit carbonic anhydrase [see Drug Interactions (7)] . Advise patients to increase fluid intake (to increase urinary output), which may decrease the concentration of substances involved in kidney stone formation.

5.11 Oligohidrosis and Hyperthermia

Oligohidrosis (decreased sweating), infrequently resulting in hospitalization, has been reported in association with the use of topiramate. Decreased sweating and an elevation in body temperature above normal characterized these cases. Some of the cases have been reported with topiramate after exposure to elevated environmental temperatures.

The majority of the reports associated with topiramate have been in pediatric patients. Advise all patients and caregivers to monitor for decreased sweating and increased body temperature during physical activity, especially in hot weather. Patients on concomitant medications that predispose them to heat-related disorders may be at increased risk.

5.12 Hypokalemia

QSYMIA can increase the risk of hypokalemia through its inhibition of carbonic anhydrase activity. In addition, when QSYMIA is used in conjunction with non-potassium sparing diuretics this may further potentiate potassium-wasting. Measure potassium before and during treatment with QSYMIA [see Adverse Reactions (6.1), Drug Interactions (7), and Clinical Pharmacology (12.3)] .

5.13 Serious Skin Reactions

Serious skin reactions (Stevens-Johnson Syndrome [SJS] and Toxic Epidermal Necrolysis [TEN]) have been reported in patients receiving topiramate. QSYMIA should be discontinued at the first sign of a rash, unless the rash is clearly not drug-related. If signs or symptoms suggest SJS/TEN, use of this drug should not be resumed, and alternative therapy should be considered. Inform patients about the signs of serious skin reactions.

5.14 Allergic Reactions Due to Inactive Ingredient FD&C Yellow No. 5

This product contains FD&C Yellow No. 5 (tartrazine) which may cause allergic-type reactions (including bronchial asthma) in certain susceptible persons. Although the overall incidence of FD&C Yellow No. 5 (tartrazine) sensitivity in the general population is low, it is frequently seen in patients who also have aspirin hypersensitivity.

6 ADVERSE REACTIONS

The following clinically significant adverse reactions are described elsewhere in the labeling:

- Embryo-Fetal Toxicity [see Warnings and Precautions (5.1) and Use in Specific Populations (8.1, 8.6)]
- Suicidal Behavior and Ideation [see Warnings and Precautions (5.2)]
- Risk of Ophthalmologic Adverse Reactions [see Warnings and Precautions (5.3)]
- Mood and Sleep Disorders [see Warnings and Precautions (5.4)]
- Cognitive Impairment [see Warnings and Precautions (5.5)]
- Slowing of Linear Growth [see Warnings and Precautions (5.6)]
- Metabolic Acidosis [see Warnings and Precautions (5.7)]
- Decrease in Renal Function [see Warnings and Precautions (5.8)]
- Risk of Seizures with Abrupt Withdrawal of QSYMIA [see Warnings and Precautions (5.9)]
- Kidney Stones [see Warnings and Precautions (5.10)]
- Oligohydrosis and Hyperthermia [see Warnings and Precautions (5.11)]
- Hypokalemia [see Warnings and Precautions (5.12)]
- Serious Skin Reactions [see Warnings and Precautions (5.13)]

6.1 Clinical Trials Experience

Because clinical trials are conducted under widely varying conditions, adverse reaction rates observed in the clinical trials of a drug cannot be directly compared to rates in the clinical studies of another drug and may not reflect the rates observed in practice.

The data described herein reflect exposure to QSYMIA in two 1-year, randomized, double-blind, placebo-controlled, multicenter clinical trials and two supportive trials in 2,318 adult patients with overweight or obesity [936 (40%) patients with hypertension, 309 (13%) patients with type 2 diabetes mellitus, 808 (35%) patients with BMI greater than 40 kg/m^2] exposed for a mean duration of 298 days. Data in this section also describe adverse reactions from a 1-year, randomized, double-blind, placebo-controlled multicenter clinical trial that evaluated 223 pediatric patients (12 to 17 years old) with obesity [see Clinical Studies (14)] .

Adults

Adverse reactions occurring at greater than or equal to 5% and at least 1.5 times placebo in adults include paraesthesia, dizziness, dysgeusia, insomnia, constipation, and dry mouth.

Adverse reactions reported in greater than or equal to 2% of QSYMIA-treated adults and more frequently than in the placebo group are shown in Table 1.

Table 1. Adverse Reactions Reported in ≥2% of QSYMIA-Treated Adults with Overweight or Obesity and More Frequently than Placebo in Overall Study Population of 1 Year Duration
Adverse Reaction | Placebo (N = 1561) % | QSYMIA 3.75 mg/23 mg (N = 240) % | QSYMIA 7.5 mg/46 mg (N = 498) % | QSYMIA 15 mg/92 mg (N = 1,580) %
Paraesthesia | 2 | 4 | 14 | 20
Dry Mouth | 3 | 7 | 14 | 19
Constipation | 6 | 8 | 15 | 16
Upper Respiratory Tract Infection | 13 | 16 | 12 | 14
Headache | 9 | 10 | 7 | 11
Dysgeusia | 1 | 1 | 7 | 9
Insomnia | 5 | 5 | 6 | 9
Nasopharyngitis | 8 | 13 | 11 | 9
Dizziness | 3 | 3 | 7 | 9
Sinusitis | 6 | 8 | 7 | 8
Nausea | 4 | 6 | 4 | 7
Back Pain | 5 | 5 | 6 | 7
Fatigue | 4 | 5 | 4 | 6
Diarrhea | 5 | 5 | 6 | 6
Vision Blurred | 4 | 6 | 4 | 5
Bronchitis | 4 | 7 | 4 | 5
Urinary Tract Infection | 4 | 3 | 5 | 5
Cough | 4 | 3 | 4 | 5
Influenza | 4 | 8 | 5 | 4
Depression | 2 | 3 | 3 | 4
Anxiety | 2 | 3 | 2 | 4
Hypoesthesia | 1 | 1 | 4 | 4
Irritability | 1 | 2 | 3 | 4
Alopecia | 1 | 2 | 3 | 4
Disturbance in Attention | 1 | 0 | 2 | 4
Pain in Extremity | 3 | 2 | 3 | 3
Muscle Spasms | 2 | 3 | 3 | 3
Dyspepsia | 2 | 2 | 2 | 3
Gastroesophageal Reflux Disease | 1 | 1 | 3 | 3
Rash | 2 | 2 | 2 | 3
Hypokalemia | 0 | 0 | 1 | 3
Dry Eye | 1 | 1 | 1 | 3
Gastroenteritis | 2 | 1 | 2 | 3
Pharyngolaryngeal Pain | 2 | 3 | 1 | 2
Paraesthesia Oral | 0 | 0 | 1 | 2
Eye Pain | 1 | 2 | 2 | 2
Nasal Congestion | 1 | 2 | 1 | 2
Thirst | 1 | 2 | 2 | 2
Sinus Congestion | 2 | 3 | 3 | 2
Procedural Pain | 2 | 2 | 2 | 2
Palpitations | 1 | 1 | 2 | 2
Musculoskeletal Pain | 1 | 1 | 3 | 2
Decreased Appetite | 1 | 2 | 2 | 2
Neck Pain | 1 | 1 | 2 | 1
Dysmenorrhea | 0 | 2 | 0 | 1
Chest Discomfort | 0 | 2 | 0 | 1

Pediatric Patients Aged 12 Years and Older

Adverse reactions occurring in pediatric patients treated with either QSYMIA 15 mg/92 mg or QSYMIA 7.5 mg/46 mg at greater than or equal to 4% and higher than placebo include depression, pyrexia, dizziness, arthralgia, influenza, and ligament sprain.

Adverse reactions reported in greater than or equal to 2% of QSYMIA-treated pediatric patients and more frequently than in the placebo group from a study in pediatric patients aged 12 years and older are shown in Table 2.

Table 2. Adverse Reactions Reported in ≥2% of QSYMIA-Treated Pediatric Patients Aged 12 to 17 Years and More Frequently than Placebo during 56 Weeks of Treatment
Adverse Reaction | Placebo (N = 56) % | QSYMIA 7.5 mg/46 mg (N = 54) % | QSYMIA 15 mg/92 mg (N = 113) %
Depression | 0 | 2 | 4
Nausea | 4 | 4 | 4
Pyrexia | 2 | 2 | 4
Dizziness | 0 | 2 | 4
Arthralgia | 0 | 2 | 4
Paraesthesia | 0 | 2 | 3
Anxiety | 0 | 2 | 3
Abdominal Pain Upper | 0 | 0 | 3
Fatigue | 2 | 0 | 3
Ear Infection | 0 | 2 | 3
Musculoskeletal Chest Pain | 0 | 0 | 3
Influenza | 0 | 4 | 2
Ligament Sprain | 0 | 4 | 2

Increase in Heart Rate

In adult and pediatric clinical trials, there was a higher incidence of heart rate elevations observed in QSYMIA-treated compared to placebo-treated patients. In an 8-week ambulatory blood pressure monitoring (ABPM) study in adults, QSYMIA increased the 24-hr average heart rate by 3.6 beats per minute (bpm) (95% CI 2.1, 5.2) compared to the placebo group [see Clinical Pharmacology (12.2)] .

In clinical trials, a higher percentage of QSYMIA-treated adults and pediatric patients aged 12 years and older experienced heart rate increases from baseline of more than 5, 10, 15, and 20 bpm compared to placebo-treated patients. Table 3 and Table 4 provide the numbers and percentages of adult and pediatric patients, respectively, with elevations in heart rate in clinical studies of up to one year.

Table 3. Number and Percentage of Adults with Overweight or Obesity with an Increase in Heart Rate at a Single Time Point from Baseline
 | Placebo N=1561 n (%) | QSYMIA 3.75 mg/23 mg N=240 n (%) | QSYMIA 7.5 mg/46 mg N=498 n (%) | QSYMIA 15 mg/92 mg N=1580 n (%)
Greater than 5 bpm | 1021 (65.4) | 168 (70.0) | 372 (74.7) | 1228 (77.7)
Greater than 10 bpm | 657 (42.1) | 120 (50.0) | 251 (50.4) | 887 (56.1)
Greater than 15 bpm | 410 (26.3) | 79 (32.9) | 165 (33.1) | 590 (37.3)
Greater than 20 bpm | 186 (11.9) | 36 (15.0) | 67 (13.5) | 309 (19.6)

Table 4. Number and Percentage of Pediatric Patients with an Increase in Heart Rate at a Single Time Point from Baseline
 | Placebo N=56 n (%) | QSYMIA 7.5 mg/46 mg N=54 n (%) | QSYMIA 15 mg/92 mg N=113 n (%)
Greater than 5 bpm | 37 (66.1) | 38 (70.4) | 92 (81.4)
Greater than 10 bpm | 26 (46.4) | 30 (55.6) | 73 (64.6)
Greater than 15 bpm | 17 (30.4) | 18 (33.3) | 48 (42.5)
Greater than 20 bpm | 10 (17.9) | 10 (18.5) | 27 (23.9)

Paraesthesia/Dysgeusia

In adult clinical trials, reports of paraesthesia, characterized as tingling in hands, feet, or face, and dysgeusia, characterized as a metallic taste, occurred (see Table 1). Adverse reactions of paraesthesia were also reported in pediatric patients (see Table 2). QSYMIA-treated adult patients discontinued treatment due to these adverse reactions (1% for paraesthesia and 0.6% for dysgeusia); no pediatric patients discontinued treatment due to paraesthesia or dysgeusia.

Mood and Sleep Disorders

The proportion of adult patients in 1-year controlled trials of QSYMIA reporting one or more adverse reactions related to mood and sleep disorders was 15% and 21% with QSYMIA 7.5 mg/46 mg and 15 mg/92 mg, respectively, compared to 10% with placebo. These events were further categorized into sleep disorders, anxiety, and depression. Reports of sleep disorders were typically characterized as insomnia and occurred in 8.1% and 11% of patients treated with QSYMIA 7.5 mg/46 mg and 15 mg/92 mg, respectively, compared to 5.8% of patients treated with placebo. Reports of anxiety occurred in 4.8% and 7.9% of patients treated with QSYMIA 7.5 mg/46 mg and 15 mg/92 mg, respectively, compared to 2.6% of patients treated with placebo. Reports of depression/mood problems occurred in 3.8% and 7.6% of patients treated with QSYMIA 7.5 mg/46 mg and 15 mg/92 mg, respectively, compared to 3.4% of patients treated with placebo. Mood and sleep disorder adverse reactions occurred in patients with and without a history of depression.

In a pediatric clinical trial, higher proportions of QSYMIA-treated patients reported one or more adverse reactions related to mood (e.g., depression, anxiety) and sleep disorders (e.g., insomnia) compared to placebo-treated patients (see Table 2).

Cognitive Disorders

In the 1-year controlled trials of QSYMIA in adults, the proportion of patients who experienced one or more cognitive-related adverse reactions was 5.0% for QSYMIA 7.5 mg/46 mg and 7.6% for QSYMIA 15 mg/92 mg, compared to 1.5% for placebo. These adverse reactions were comprised primarily of reports of problems with attention/concentration, memory, and language (word-finding). These events occurred at any time during treatment with QSYMIA.

Slowing of Linear Growth

QSYMIA is associated with a reduction in height velocity (centimeters of height gained per year) in obese pediatric patients 12 to 17 years of age. In a 56-week study, average height increased from baseline in both QSYMIA- and placebo-treated patients; however, a lower height velocity of -1.3 to -1.4 cm/year was observed in QSYMIA-treated compared to placebo-treated patients.

Decrease in Bone Mineral Density

QSYMIA is associated with less bone mineral acquisition in pediatric patients 12 to 17 years of age. In a substudy (n=66) evaluating bone mineralization via dual-energy X-ray absorptiometry (DEXA), increases in bone mineral density (BMD) at the lumbar spine and total body less head (TBLH) were smaller in pediatric patients treated with QSYMIA compared to those treated with placebo after 1 year of treatment. Declines in BMD Z-scores of -0.5 or greater from baseline for TBLH were observed in 9% of QSYMIA 7.5 mg/46 mg-treated patients and 30% of QSYMIA 15 mg/92 mg-treated patients, compared to 0% of placebo-treated patients. The sample size and study duration were too small to determine if fracture risk is increased. Decreased BMD was not correlated with decreased serum bicarbonate, which commonly occurs with QSYMIA treatment, or changes in body weight. No patient had a BMD Z-score that went below -2.0 during the trial. Similar findings were observed in a 1 year, active-controlled trial of topiramate in pediatric patients with another condition.

Nephrolithiasis

In the 1-year controlled trials of QSYMIA in adults, the incidence of nephrolithiasis was 0.2% for QSYMIA 7.5 mg/46 mg and 1.2% for QSYMIA 15 mg/92 mg, compared to 0.3% for placebo.

Laboratory Abnormalities

Serum Bicarbonate

In the 1-year controlled trials of QSYMIA in adults, the incidence of persistent decreases in serum bicarbonate below the normal range (levels of less than 21 mEq/L at 2 consecutive visits or at the final visit) was 6.4% for QSYMIA 7.5 mg/46 mg and 12.8% for QSYMIA 15 mg/92 mg, compared to 2.1% for placebo. The incidence of persistent, markedly low serum bicarbonate values (levels of less than 17 mEq/L on 2 consecutive visits or at the final visit) was 0.2% for QSYMIA 7.5 mg/46 mg dose and 0.7% for QSYMIA 15 mg/92 mg dose, compared to 0.1% for placebo. In a pediatric clinical trial, 60 to 70% QSYMIA-treated patients had a persistent bicarbonate level below the normal range (<21 mEq/L) compared to 43% of placebo-treated patients.

Serum Potassium

In the 1-year controlled trials of QSYMIA in adults, the incidence of persistent low serum potassium values (less than 3.5 mEq/L at two consecutive visits or at the final visit) during the trial was 3.6% for QSYMIA 7.5 mg/46 mg dose and 4.9% for QSYMIA 15 mg/92 mg, compared to 1.1% for placebo. Of the subjects who experienced persistent low serum potassium, 88% were receiving treatment with a non-potassium sparing diuretic.

The incidence of markedly low serum potassium (less than 3 mEq/L, and a reduction from pre-treatment of greater than 0.5 mEq/L) at any time during the trial was 0.2% for QSYMIA 7.5 mg/46 mg dose and 0.7% for QSYMIA 15 mg/92 mg dose, compared to 0.0% for placebo. Persistent markedly low serum potassium (less than 3 mEq/L, and a reduction from pre-treatment of greater than 0.5 mEq/L at two consecutive visits or at the final visit) occurred in 0.2% receiving QSYMIA 7.5 mg/46 mg dose and 0.1% receiving QSYMIA 15 mg/92 mg dose, compared to 0.0% receiving placebo.

Low serum potassium levels (<3.5 mEq/L) were not observed in a 56-week clinical trial of pediatric patients with obesity.

Serum Creatinine

In the 1-year controlled trials of QSYMIA in adults and pediatric patients, there was an increase in serum creatinine from baseline, peaking between Week 4 to 8 in adults and at Week 16 in pediatric patients. Serum creatinine values declined but remained elevated over baseline over 1 year of treatment. The incidence of increases in serum creatinine of greater than or equal to 0.3 mg/dL at any time during treatment in adults was 7.2% for QSYMIA 7.5 mg/46 mg and 8.4% for QSYMIA 15 mg/92 mg, compared to 2.0% for placebo; 17% of pediatric patients treated with QSYMIA 7.5 mg/46 mg or QSYMIA 15 mg/92 mg and 0% of patients treated with placebo had a serum creatinine ≥0.3 mg/dL at any time post-randomization. Increases in serum creatinine of greater than or equal to 50% over baseline occurred in 2.0% of adult subjects receiving QSYMIA 7.5 mg/46 mg and 2.8% receiving QSYMIA 15 mg/92 mg, compared to 0.6% receiving placebo.

Serum Ammonia

Hyperammonemia with or without encephalopathy has been reported with topiramate. The risk for hyperammonemia with topiramate appears dose related and has been reported more frequently when concomitantly used with valproic acid [see Drug Interactions (7)] .

The incidence of hyperammonemia in pediatric patients 12 to 17 years of age in clinical trials of another condition was 26% in patients taking topiramate at 100 mg/day (1.1 times the maximum recommended dosage of QSYMIA) and 14% in patients taking topiramate at 50 mg/day (0.6 times the maximum recommended dosage of QSYMIA), compared to 9% in patients taking placebo. There was also an increased incidence of markedly increased hyperammonemia (defined as 50% above the upper limit of normal reference range) at the 100 mg dose.

6.2 Postmarketing Experience

The following adverse reactions have been reported during post approval use of QSYMIA, phentermine, and topiramate. Because these reactions are reported voluntarily from a population of uncertain size it is not always possible to reliably estimate their frequency or establish a causal relationship to drug exposure.

QSYMIA

Psychiatric:suicidal ideation, suicidal behavior

Ophthalmic:acute angle closure glaucoma, increased intraocular pressure

Phentermine

Allergic Reactions:urticaria

Cardiovascular:elevation of blood pressure, ischemic events

Central Nervous System:euphoria, psychosis, tremor

Reproductive:changes in libido, impotence

Topiramate

Dermatologic:bullous skin reactions (including erythema multiforme, Stevens-Johnson syndrome, toxic epidermal necrolysis), pemphigus

Gastrointestinal:pancreatitis

Hepatic:hepatic failure (including fatalities), hepatitis

Metabolic:hyperammonemia with or without encephalopathy has been reported with concomitant valproic acid [see Drug Interactions (7)] , hypothermia

Ophthalmic:maculopathy

7 DRUG INTERACTIONS

Table 5 displays clinically significant drug interactions with QSYMIA.

Table 5. Clinically Significant Drug Interactions with QSYMIA
Monoamine Oxidase Inhibitors
Clinical Impact | Concomitant use of phentermine with monoamine oxidase inhibitors (MAOIs) increases the risk of hypertensive crisis.
Intervention | Concomitant use of QSYMIA is contraindicated during MAOI treatment and within 14 days of stopping an MAOI.
Oral Contraceptives
Clinical Impact | Co-administration of multiple-dose QSYMIA 15 mg/92 mg once daily with a single dose of oral contraceptive containing 35 µg ethinyl estradiol (estrogen component) and 1 mg norethindrone (progestin component), in obese otherwise healthy volunteers, decreased the exposure of ethinyl estradiol by 16% and increased the exposure of norethindrone by 22% [see Clinical Pharmacology (12.3)] . Although this interaction is not anticipated to increase the risk of pregnancy, irregular bleeding (spotting) may occur more frequently due to both the increased exposure to the progestin and lower exposure to the estrogen, which tends to stabilize the endometrium.
Intervention | Inform patients not to discontinue their combination oral contraceptive if spotting occurs, but to notify their health care provider if the spotting is troubling to them.
CNS Depressants Including Alcohol
Clinical Impact | The concomitant use of alcohol or CNS depressant drugs (e.g., barbiturates, benzodiazepines, and sleep medications) with phentermine or topiramate may potentiate CNS depression such as dizziness or cognitive adverse reactions, or other centrally mediated effects of these agents.
Intervention | Advise patients not to drive or operate machinery until they have gained sufficient experience on QSYMIA to gauge whether it adversely affects their mental performance, motor performance, and/or vision. Caution patients against excessive alcohol intake when taking QSYMIA. Consider QSYMIA dosage reduction or discontinuation if cognitive dysfunction persists [see Warnings and Precautions (5.5)].
Non-Potassium Sparing Diuretics
Clinical Impact | Concurrent use of QSYMIA with non-potassium sparing diuretics may potentiate the potassium-wasting action of these diuretics. Concomitant administration of hydrochlorothiazide alone with topiramate alone has been shown to increase the Cmax and AUC of topiramate by 27% and 29%, respectively.
Intervention | When QSYMIA is used concomitantly with non-potassium-sparing diuretics, measure potassium before and during QSYMIA treatment [see Warnings and Precautions (5.12) and Clinical Pharmacology (12.3)] .
Antiepileptic Drugs
Clinical Impact | Concomitant administration of phenytoin or carbamazepine with topiramate in patients with epilepsy, decreased plasma concentrations of topiramate by 48% and 40%, respectively, when compared to topiramate given alone [see Clinical Pharmacology (12.3)] . Concomitant administration of valproic acid and topiramate has been associated with hyperammonemia with and without encephalopathy. Concomitant administration of topiramate with valproic acid in patients has also been associated with hypothermia (with and without hyperammonemia).
Intervention | Consider measuring blood ammonia in patients in whom the onset of hypothermia or encephalopathy has been reported [see Clinical Pharmacology (12.3)] .
Carbonic Anhydrase Inhibitors
Clinical Impact | Concomitant use of topiramate with any other carbonic anhydrase inhibitor may increase the severity of metabolic acidosis and may also increase the risk of kidney stone formation.
Intervention | Avoid the use of QSYMIA with other drugs that inhibit carbonic anhydrase. If concomitant use of QSYMIA with another carbonic anhydrase inhibitor is unavoidable, monitor patient for the appearance or worsening of metabolic acidosis [see Warnings and Precautions (5.7, 5.10)] .
Pioglitazone
Clinical Impact | A decrease in the exposure of pioglitazone and its active metabolites were noted with the concurrent use of pioglitazone and topiramate in a clinical trial. The clinical relevance of these observations is unknown.
Intervention | Consider increased glycemic monitoring when using pioglitazone and QSYMIA concomitantly [see Clinical Pharmacology (12.3)] .
Amitriptyline
Clinical Impact | Some patients may experience a large increase in amitriptyline concentration in the presence of topiramate.
Intervention | Any adjustments in amitriptyline dose when used with QSYMIA should be made according to the patient's clinical response and not on the basis of amitriptyline levels [see Clinical Pharmacology (12.3)] .

8 USE IN SPECIFIC POPULATIONS

8.1 Pregnancy

Risk Summary

QSYMIA is contraindicated in pregnant patients. The use of QSYMIA can cause fetal harm, and weight loss offers no clear clinical benefit to a pregnant patient (see Clinical Considerations) . Available data from pregnancy registries and epidemiologic studies indicate an increased risk of major congenital malformations, including but not limited to cleft lip and/or cleft palate (oral clefts), and of being SGA in infants exposed in uteroto topiramate (see Data) . When phentermine and topiramate were co-administered to rats at doses of 3.75 and 25 mg/kg, respectively [approximately 2 times the maximum recommended human dose (MRHD) based on area under the curve (AUC)], or at the same dose to rabbits (approximately 0.1 times and 1 time, respectively, the clinical exposures at the MRHD based on AUC), there were no drug-related malformations. However, structural malformations, including craniofacial defects and reduced fetal weights occurred in offspring of multiple species of pregnant animals administered topiramate at clinically relevant doses (see Data) . Advise pregnant women of the potential risk to a fetus.

Clinical Considerations

Disease Associated Maternal and/or Embryo/Fetal Risk

Weight loss during pregnancy may result in fetal harm. Appropriate weight gain based on pre-pregnancy weight is currently recommended for all pregnant patients, including those who are already overweight or obese, due to the obligatory weight gain that occurs in maternal tissues during pregnancy. Maternal obesity increases the risk for congenital malformations, including neural tube defects, cardiac malformations, oral clefts, and limb reduction defects.

Fetal/Neonatal Adverse Reactions

QSYMIA can cause metabolic acidosis [see Warnings and Precautions (5.7)] . The effect of topiramate-induced metabolic acidosis has not been studied in pregnancy; however, metabolic acidosis in pregnancy (due to other causes) can cause decreased fetal growth, decreased fetal oxygenation, and fetal death, and may affect the fetus' ability to tolerate labor.

Data

Human Data

Data evaluating the risk of major congenital malformations, oral clefts, and being SGA with topiramate exposure during pregnancy is available from the North American Antiepileptic Drug (NAAED) Pregnancy Registry and from several larger retrospective epidemiologic studies.

Major Congenital Malformations

The NAAED Pregnancy Registry indicates an increased risk of major congenital malformations, including but not limited to oral clefts in infants exposed to topiramate during the first trimester of pregnancy. Other than oral clefts, no specific pattern of major congenital malformations or grouping of major congenital malformation types were observed. In the NAAED pregnancy registry, when topiramate-exposed infants with only oral clefts were excluded, the prevalence of major congenital malformations (4.1%) was higher than that in infants exposed to a reference antiepileptic drug (AED) (1.8%) or in infants with mothers without epilepsy and without exposure to AEDs (1.1%).

Oral Clefts

In the NAAED Pregnancy Registry, the prevalence of oral clefts among topiramate-exposed infants (1.4%) was higher than the prevalence in infants exposed to a reference AED (0.3%) or the prevalence in infants with mothers without epilepsy and without exposure to AEDs (0.11%). It was also higher than the background prevalence in United States (0.17%) as estimated by the Centers for Disease Control and Prevention (CDC). The relative risk of oral clefts in topiramate-exposed pregnancies in the NAAED Pregnancy Registry was 12.5 (95% Confidence Interval [CI] 5.9-26.37) as compared to the risk in a background population of untreated women. The UK Epilepsy and Pregnancy Register reported a prevalence of oral clefts among infants exposed to topiramate monotherapy (3.2%) that was 16 times higher than the background rate in the UK (0.2%).

Larger retrospective epidemiology studies showed that topiramate monotherapy exposure in pregnancy is associated with an approximately two to five-fold increased risk of oral clefts. The FORTRESS study found an excess risk of 1.5 (95% CI = -1.1 to 4.1) oral cleft cases per 1,000 infants exposed to topiramate during the first trimester.

Small for Gestational Age

Data from the NAAED Pregnancy Registry and population-based birth registry cohort indicate that exposure to topiramate in utero is associated with an increased risk of SGA newborns (birth weight <10th percentile). In the NAAED Pregnancy Registry, 19.7% of topiramate-exposed newborns were SGA compared to 7.9% of newborns exposed to a reference AED and 5.4% of newborns of mothers without epilepsy and without AED exposure. In the medical Birth Registry of Norway, a population-based pregnancy registry, 25% of newborns in the topiramate monotherapy exposure group were SGA compared to 9% in the comparison group unexposed to AEDs. The long-term consequences of the SGA findings are not known.

Animal Data

Phentermine/Topiramate

Embryo-fetal development studies have been conducted in rats and rabbits with combination phentermine and topiramate treatment. Phentermine and topiramate co-administered to rats during the period of organogenesis (gestation day (GD) 6 through 17) caused reduced fetal body weights but did not cause fetal malformations at the maximum dose of 3.75 mg/kg phentermine and 25 mg/kg topiramate [approximately 2 times the maximum recommended human dose (MRHD) based on area under the curve (AUC) estimates for each active ingredient]. In a similar study in rabbits in which the same doses were administered from GD 6 through 18, no effects on embryo-fetal development were observed at approximately 0.1 times (phentermine) and 1 time (topiramate) clinical exposures at the MRHD based on AUC. Significantly lower maternal body weight gain was recorded at these doses in rats and rabbits.

A pre- and post-natal development study was conducted in rats with combination phentermine and topiramate treatment. There were no adverse maternal or offspring effects in rats treated throughout organogenesis and lactation with 1.5 mg/kg/day phentermine and 10 mg/kg/day topiramate (approximately 2- and 3-times clinical exposures at the MRHD, respectively, based on AUC). Treatment with higher doses of 11.25 mg/kg/day phentermine and 75 mg/kg/day topiramate (approximately 5 and 6 times maximum clinical doses based on AUC, respectively) caused reduced maternal body weight gain and offspring toxicity. Offspring effects included lower pup survival after birth, increased limb and tail malformations, reduced pup body weight and delayed growth, development, and sexual maturation without affecting learning, memory, or fertility and reproduction. The limb and tail malformations were consistent with results of animal studies conducted with topiramate alone.

Phentermine

Animal reproduction studies have not been conducted with phentermine. Limited data from studies conducted with the phentermine/topiramate combination indicate that phentermine alone was not teratogenic but resulted in lower body weight and reduced survival of offspring in rats at 5-fold the MRHD of QSYMIA, based on AUC.

Topiramate

Topiramate causes developmental toxicity, including teratogenicity, at clinically relevant doses in multiple animal species.

Developmental toxicity, including teratogenicity, occurred at clinically relevant doses in multiple animal species in which topiramate was administered during the period of organogenesis (GD 6 – 15 in rodents, GD 6 – 18 in rabbits. In these studies, fetal malformations (primarily craniofacial defects such as cleft palate), limb malformations (ectrodactyly, micromelia, and amelia), rib/vertebral column anomalies, and/or reduced fetal weights were observed at dosages ≥ 20 mg/kg in mice (approximately 2 times the MRHD of topiramate in QSYMIA 15 mg/92 mg on a mg/m^2 basis), 20 mg/kg in rats (2 times the MRHD of QSYMIA based on estimated AUC), and 35 mg/kg in rabbits (2 times the MRHD based on estimated AUC). When rats were administered topiramate from GD 15 through lactation day 20, reductions in pre- and/or post-weaning weights occurred at dosages ≥ 2 mg/kg (2 times the MRHD of QSYMIA based on estimated AUC).

8.2 Lactation

Risk Summary

Topiramate and phentermine are present in human milk. There are no data on the effects of topiramate and phentermine on milk production. Diarrhea and somnolence have been reported in breastfed infants with maternal use of topiramate. There are no data on the effects of phentermine in breastfed infants. Because of the potential for serious adverse reactions, including changes in sleep, irritability, hypertension, vomiting, tremor, and weight loss in breastfed infants with maternal use of phentermine, advise patients that breastfeeding is not recommended during QSYMIA therapy.

8.3 Females and Males of Reproductive Potential

Pregnancy Testing

Pregnancy testing is recommended in patients who can become pregnant before initiating QSYMIA and monthly during QSYMIA therapy [see Warnings and Precautions (5.1) and Use in Specific Populations (8.1)] .

Contraception

Females

QSYMIA can cause fetal harm when administered to a pregnant patient [see Use in Specific Populations (8.1)] . Advise patients who can become pregnant to use effective contraception during therapy with QSYMIA.

For patients taking combined oral contraceptives (COCs), use of QSYMIA may cause irregular bleeding [see Drug Interactions (7)] . Advise patients not to discontinue taking their COC and to contact their health care provider.

8.4 Pediatric Use

The safety and effectiveness of QSYMIA as an adjunct to a reduced-calorie diet and increased physical activity for weight reduction and long-term maintenance of body weight have been established in pediatric patients aged 12 years and older with obesity. Use of QSYMIA for this indication is supported by a 56-week, double-blind, placebo-controlled study in 223 pediatric patients aged 12 years and above, a pharmacokinetic study in pediatric patients, and studies in adults with obesity [see Clinical Pharmacology (12.3)and Clinical Studies (14)] .

In a pediatric clinical trial, there was one episode of serious suicidal ideation in a QSYMIA-treated patient requiring hospitalization and pharmacologic treatment [see Warnings and Precautions (5.2)] more patients treated with QSYMIA versus placebo reported adverse reactions related to mood (e.g., depression, anxiety) and sleep disorders (e.g., insomnia) [see Warnings and Precautions (5.4)] . Increases in bone mineral density and linear growth were attenuated in QSYMIA- versus placebo-treated patients [see Warnings and Precautions (5.6)] . Serious adverse reactions seen in pediatric patients using topiramate include acute angle glaucoma, oligohidrosis and hyperthermia, metabolic acidosis, cognitive and neuropsychiatric reactions, hyperammonemia and encephalopathy, and kidney stones.

The safety and effectiveness of QSYMIA in pediatric patients below the age of 12 years have not been established.

8.5 Geriatric Use

In the QSYMIA clinical trials, a total of 254 (7%) of the patients were 65 to 69 years of age; no patients 70 years of age or older were enrolled.

Clinical studies of QSYMIA did not include sufficient numbers of patients aged 65 and over to determine whether they respond differently from younger patients. In general, dose selection for an elderly patient should be cautious, usually starting at the low end of the dosing range, reflecting the greater frequency of decreased hepatic, renal, or cardiac function, and of concomitant disease or other drug therapy.

8.6 Renal Impairment

Compared to healthy volunteers with normal renal function, patients with moderate and severe renal impairment as estimated by the Cockcroft-Gault equation had higher exposures to phentermine and topiramate.

The recommended dosage of QSYMIA in patients with mild renal impairment (CrCl greater or equal to 50 and less than 80 mL/min) is the same as the recommended dosage for patients with normal renal function.

In patients with moderate (CrCl greater than or equal to 30 to less than 50 mL/min) and severe (CrCl less than 30 mL/min) renal impairment, the maximum recommended dosage is QSYMIA 7.5 mg/46 mg once daily.

QSYMIA has not been studied in patients with end-stage renal disease on dialysis. Avoid QSYMIA in this patient population [see Dosage and Administration (2.4) and Clinical Pharmacology (12.3)] .

8.7 Hepatic Impairment

In patients with mild (Child-Pugh 5 - 6) and moderate (Child-Pugh 7 - 9) hepatic impairment, exposure to phentermine was higher compared to healthy volunteers with normal hepatic function. Exposure to topiramate was similar among patients with mild and moderate hepatic impairment and healthy volunteers.

The recommended dosage of QSYMIA in patients with mild hepatic impairment (Child-Pugh 5 - 6) is the same as the recommended dosage in patients with normal hepatic function.

In patients with moderate hepatic impairment, the maximum recommended dosage is QSYMIA 7.5 mg/46 mg once daily.

QSYMIA has not been studied in patients with severe hepatic impairment (Child-Pugh score 10 - 15). Avoid QSYMIA in this patient population [see Dosage and Administration (2.5) and Clinical Pharmacology (12.3)] .

9 DRUG ABUSE AND DEPENDENCE

9.1 Controlled Substance

QSYMIA contains phentermine, a Schedule IV controlled substance, and topiramate, which is not a controlled substance.

9.2 Abuse

Phentermine has a known potential for abuse. Abuse is the intentional, non-therapeutic use of a drug, even once, for its desirable psychological or physiological effects.

Phentermine is related chemically and pharmacologically to amphetamines. Amphetamines and other stimulant drugs have been extensively abused. Abuse of amphetamines and related drugs (e.g., phentermine) may be associated with impaired control over drug use and severe social dysfunction. There are reports of patients who have increased the dosage of these drugs to many times higher than recommended. Assess the risk of abuse prior to prescribing QSYMIA as part of a weight reduction and long-term maintenance of body weight program.

9.3 Dependence

Physical dependence may occur in patients treated with QSYMIA. Physical dependence is a state that develops as a result of physiological adaptation in response to repeated drug use, manifested by withdrawal signs and symptoms after abrupt discontinuation or a significant dose reduction of a drug.

The following adverse reactions have been associated with the abrupt discontinuation of the individual components of QSYMIA:

- For topiramate, abrupt discontinuation has been associated with seizures in patients without a history of seizures or epilepsy [see Warnings and Precautions (5.9)] .
- For phentermine, abrupt discontinuation following prolonged high dosage administration results in extreme fatigue and mental depression; changes are also noted on a sleep electroencephalogram.

Thus, in situations where rapid withdrawal of QSYMIA is required, appropriate medical monitoring is recommended. Patients discontinuing QSYMIA 15 mg/92 mg should be gradually tapered to reduce the possibility of precipitating a seizure [see Dosage and Administration (2.3)] .

10 OVERDOSAGE

In the event of a significant overdose with QSYMIA, if the ingestion is recent, the stomach should be emptied immediately by gastric lavage or by induction of emesis. Appropriate supportive treatment should be provided according to the patient's clinical signs and symptoms. In the event of an overdose of QSYMIA, consider contacting the Poison Help line (1-800-222-1222) or a medical toxicologist for additional overdosage management recommendations.

Acute overdose of phentermine may be associated with restlessness, tremor, hyperreflexia, rapid respiration, confusion, aggressiveness, hallucinations, and panic states. Fatigue and depression usually follow the central stimulation. Cardiovascular effects include arrhythmia, hypertension or hypotension, and circulatory collapse. Gastrointestinal symptoms include nausea, vomiting, diarrhea, and abdominal cramps. Fatal poisoning usually terminates in convulsions and coma. Manifestations of chronic intoxication with anorectic drugs include severe dermatoses, marked insomnia, irritability, hyperactivity, and personality changes. A severe manifestation of chronic intoxication is psychosis, often clinically indistinguishable from schizophrenia.

Management of acute phentermine intoxication is largely symptomatic and includes lavage and sedation with a barbiturate. Acidification of the urine increases phentermine excretion. Intravenous phentolamine has been suggested for possible acute, severe hypertension, if this complicates phentermine overdosage.

Topiramate overdose has resulted in severe metabolic acidosis. Other signs and symptoms include convulsions, drowsiness, speech disturbance, blurred vision, diplopia, impaired mentation, lethargy, abnormal coordination, stupor, hypotension, abdominal pain, agitation, dizziness, and depression. The clinical consequences were not severe in most cases, but deaths have been reported after overdoses involving topiramate. A patient who ingested a dose between 96 and 110 gm topiramate was admitted to hospital with coma lasting 20 to 24 hours followed by full recovery after 3 to 4 days.

Hemodialysis is an effective means of removing topiramate from the body.

11 DESCRIPTION

QSYMIA extended-release capsules are comprised of immediate-release phentermine hydrochloride (expressed as the weight of the free base) and extended-release topiramate. QSYMIA contains phentermine hydrochloride, a sympathomimetic amine anorectic, and topiramate, a sulfamate-substituted monosaccharide.

Phentermine Hydrochloride

The chemical name of phentermine hydrochloride is α,α-dimethylphenethylamine hydrochloride. The molecular formula is C10H15N ∙ HCl and its molecular weight is 185.7 (hydrochloride salt) or 149.2 (free base). Phentermine hydrochloride is a white, odorless, hygroscopic, crystalline powder that is soluble in water, methanol, and ethanol. Its structural formula is:

Topiramate

Topiramate is 2,3:4,5-di-O-isopropylidene-β-D-fructopyranose sulfamate. The molecular formula is C12H21NO8S and its molecular weight is 339.4. Topiramate is a white to off-white crystalline powder with a bitter taste. It is freely soluble in methanol and acetone, sparingly soluble in pH 9 to pH 12 aqueous solutions and slightly soluble in pH 1 to pH 8 aqueous solutions. Its structural formula is:

QSYMIA

QSYMIA (phentermine and topiramate extended-release capsules) is for oral administration and available in four dosage strengths:

- 3.75 mg/23 mg (phentermine 3.75 mg and topiramate 23 mg) (equivalent to 4.67 mg of Phentermine Hydrochloride USP).
- 7.5 mg/46 mg (phentermine 7.5 mg and topiramate 46 mg) (equivalent to 9.33 mg of Phentermine Hydrochloride USP).
- 11.25 mg/69 mg (phentermine 11.25 mg and topiramate 69 mg) (equivalent to 14.0 mg of Phentermine Hydrochloride USP).
- 15 mg/92 mg (phentermine 15 mg and topiramate 92 mg) (equivalent to 18.66 mg of Phentermine Hydrochloride USP).

Each capsule contains the following inactive ingredients: FD&C Blue #1, FD&C Red #3, FD&C Yellow #5 and #6, ethylcellulose, gelatin, methylcellulose, microcrystalline cellulose, povidone, starch, sucrose, talc, titanium dioxide, and pharmaceutical black and white inks.

12 CLINICAL PHARMACOLOGY

12.1 Mechanism of Action

Phentermine is a sympathomimetic amine with pharmacologic activity similar to the prototype drugs of this class used in obesity, amphetamine (d- and d/l-amphetamine). Drugs of this class used in obesity are commonly known as "anorectics" or "anorexigenics." The effect of phentermine on weight reduction and long-term maintenance of body weight is likely mediated by release of catecholamines in the hypothalamus, resulting in reduced appetite and decreased food consumption, but other metabolic effects may also be involved. The exact mechanism of action is not known.

The precise mechanism of action of topiramate on weight reduction and long-term maintenance of body weight is not known. Topiramate's effect on weight reduction and long-term maintenance of body weight may be due to its effects on both appetite suppression and satiety enhancement, induced by a combination of pharmacologic effects including augmenting the activity of the neurotransmitter gamma-aminobutyrate, modulation of voltage-gated ion channels, inhibition of AMPA/kainite excitatory glutamate receptors, or inhibition of carbonic anhydrase.

12.2 Pharmacodynamics

Typical actions of amphetamines include central nervous system stimulation and elevation of blood pressure. Tachyphylaxis and tolerance have been demonstrated with drugs in this class.

Cardiac Electrophysiology

The effect of QSYMIA on the QTc interval was evaluated in a randomized, double-blind, placebo- and active-controlled (400 mg moxifloxacin), and parallel group/crossover thorough QT/QTc study. A total of 54 healthy subjects were administered QSYMIA 7.5 mg/46 mg at steady state and then titrated to QSYMIA 22.5 mg/138 mg at steady state. QSYMIA 22.5 mg/138 mg [a supra-therapeutic dose resulting in a phentermine and topiramate maximum concentration (Cmax) of 4- and 3- times higher than those at QSYMIA 7.5 mg/46 mg, respectively] did not affect cardiac repolarization as measured by the change from baseline in QTc.

Glomerular Filtration Rate (GFR)

Healthy obese males and females received QSYMIA daily for 4 weeks (3.75 mg/23 mg on Days 1 to 3, 7.5 mg/46 mg on Days 4 to 6, 11.25 mg/69 mg on Days 7 to 9, and 15 mg/92 mg on Days 10 to 28). The glomerular filtration rate (GFR) of these participants was assessed via iohexol clearance. On average, GFR decreased during QSYMIA treatment and returned to baseline within 4 weeks after discontinuing QSYMIA [see Warnings and Precautions (5.8)]

Ambulatory Blood Pressure Monitoring

The effect of QSYMIA on blood pressure as measured by 24-hr ABPM was evaluated in a randomized, double-blind, 3-arm (QSYMIA, placebo, and active phentermine comparator) study of adults with obesity or overweight and at least one weight-related comorbidity. The study had a treatment duration of 8 weeks, and the primary endpoint was the change from baseline to Week 8 in mean systolic blood pressure (SBP) as measured by 24-hr ABPM.

QSYMIA 15 mg/92 mg did not demonstrate a pressor effect (see Table 6). At Week 8, placebo-adjusted mean (95% CI) treatment differences by 24-hr ABPM for QSYMIA 15 mg/92 mg were SBP -3.2 mmHg (-5.5, -0.9), DBP +1.2 mmHg (-0.2, +2.6), and heart rate (HR) +3.6 bpm (+2.1, +5.2). Placebo-adjusted mean weight loss was -3.9% (-4.9%, -3.0%) for QSYMIA 15 mg/92 mg and -3.8% (-4.7%, -2.9%) for phentermine 30 mg at Week 8.

Table 6. Ambulatory Blood Pressure Monitoring Results in Adults with Obesity or Overweight Treated with QSYMIA, Placebo, or Phentermine - Change from Baseline and Treatment Difference from Placebo and Phentermine at Week 8
APBM Measure | Change from Baseline |  |  | Treatment Difference
APBM Measure | Placebo (n=130) | QSYMIA 15 mg/ 92 mg (n=122) | Phentermine 30 mg (n=133) | Qsymia – Placebo | Qsymia - Phentermine | Phentermine - Placebo
SBP (mmHg) Mean (95% CI) | -0.1 (-2.2, +1.9) | -3.3 (-5.4, -1.2) | +1.4 (-0.7, +3.4) | -3.2 (-5.5, -0.9) | -4.7 (-7.0, -2.5) | +1.5 (-0.7, +3.7)
DBP (mmHg) Mean (95% CI) | -0.4 (-1.6, +0.9) | +0.8 (-0.4, +2.1) | +2.4 (+1.1, +3.6) | +1.2 (-0.2, +2.6) | -1.5 (-2.9, -0.2) | +2.7 (+1.4, +4.1)
HR (bpm) Mean (95% CI) | -1.0 (-2.4, +0.4) | +2.6 (+1.2, +4.0) | +6.2 (+4.8, +7.6) | +3.6 (+2.1, +5.2) | -3.6 (-5.2, -2.1) | +7.2 (+5.7, +8.8)
SBP=systolic blood pressure; DBP=diastolic blood pressure; HR=heart rate; BPM=beats per minute;
ABPM=ambulatory blood pressure monitoring; CI=confidence interval
An analysis of covariance (ANCOVA) model was used in the per protocol population (observed and single imputation data) to evaluate change from baseline and between-group differences.

12.3 Pharmacokinetics

Absorption

Phentermine

Upon oral administration of a single QSYMIA 15 mg/92 mg, the resulting mean plasma phentermine maximum concentration (Cmax), time to Cmax (Tmax), area under the concentration curve from time zero to the last time with measurable concentration (AUC0-t), and area under the concentration curve from time zero to infinity (AUC0-∞) are 49.1 ng/mL, 6 hr, 1990 ng∙hr/mL, and 2000 ng∙hr/mL, respectively. A high fat meal does not affect phentermine pharmacokinetics for QSYMIA 15 mg/92 mg. Phentermine pharmacokinetics are approximately dose-proportional from QSYMIA 3.75 mg/23 mg to phentermine 15 mg/topiramate 100 mg. Upon dosing phentermine 15 mg/topiramate 100 mg fixed dose combination capsule to steady state, the mean phentermine accumulation ratios for AUC and Cmax are both approximately 2.5.

Topiramate

Upon oral administration of a single QSYMIA 15 mg/92 mg, the resulting mean plasma topiramate Cmax, Tmax, AUC0-t, and AUC0-∞, are 1020 ng/mL, 9 hr, 61600 ng∙hr/mL, and 68000 ng∙hr/mL, respectively. A high fat meal does not affect topiramate pharmacokinetics for QSYMIA 15 mg/92 mg. Topiramate pharmacokinetics are approximately dose-proportional from QSYMIA 3.75 mg/23 mg to phentermine 15 mg/topiramate 100 mg. Upon dosing phentermine 15 mg/topiramate 100 mg fixed dose combination capsule to steady state, the mean topiramate accumulation ratios for AUC and Cmax are both approximately 4.0.

Distribution

Phentermine

Phentermine is 17.5% plasma protein bound. The estimated phentermine apparent volume of distribution (Vd/F) is 348 L via population pharmacokinetic analysis.

Topiramate

Topiramate is 15 - 41% plasma protein bound over the blood concentration range of 0.5 to 250 µg/mL. The fraction bound decreased as blood topiramate increased. The estimated topiramate Vc/F (volume of the central compartment), and Vp/F (volume of the peripheral compartment) are 50.8 L, and 13.1 L, respectively, via population pharmacokinetic analysis.

Elimination

Metabolism and Excretion

Phentermine

Phentermine has two metabolic pathways, namely p-hydroxylation on the aromatic ring and N-oxidation on the aliphatic side chain. Cytochrome P450 (CYP) 3A4 primarily metabolizes phentermine but does not show extensive metabolism. Monoamine oxidase (MAO)-A and MAO-B do not metabolize phentermine. Seventy to 80% of a dose exists as unchanged phentermine in urine when administered alone. The mean phentermine terminal half-life is about 20 hours. The estimated phentermine oral clearance (CL/F) is 8.79 L/h via population pharmacokinetic analysis.

Topiramate

Topiramate does not show extensive metabolism. Six topiramate metabolites (via hydroxylation, hydrolysis, and glucuronidation) exist, none of which constitutes more than 5% of an administered dose. About 70% of a dose exists as unchanged topiramate in urine when administered alone. The mean topiramate terminal half-life is about 65 hours. The estimated topiramate CL/F is 1.17 L/h via population pharmacokinetic analysis.

Specific Populations

Patients with Renal Impairment

A single-dose, open-label study was conducted to evaluate the pharmacokinetics of QSYMIA 15 mg/92 mg in adult patients with varying degrees of chronic renal impairment compared to healthy volunteers with normal renal function. The study included patients with renal impairment classified on the basis of creatinine clearance as mild (greater or equal to 50 and less than 80 mL/min), moderate (greater than or equal to 30 and less than 50 mL/min), and severe (less than 30 mL/min). Creatinine clearance was estimated from serum creatinine based on the Cockcroft-Gault equation.

Compared to healthy volunteers, phentermine AUC0-inf was 91%, 45%, and 22% higher in patients with severe, moderate, and mild renal impairment, respectively; phentermine Cmax was 2% to 15% higher. Compared to healthy volunteers, topiramate AUC0-inf was 126%, 85%, and 25% higher for patients with severe, moderate, and mild renal impairment, respectively; topiramate Cmax was 6% to 17% higher. An inverse relationship between phentermine or topiramate Cmax or AUC and creatinine clearance was observed.

QSYMIA has not been studied in patients with end-stage renal disease on dialysis [see Dosage and Administration (2.4) and Use in Specific Populations (8.6)] .

Patients with Hepatic Impairment

A single-dose, open-label study was conducted to evaluate the pharmacokinetics of QSYMIA 15 mg/92 mg in healthy volunteers with normal hepatic function compared with patients with mild (Child-Pugh score 5 - 6) and moderate (Child-Pugh score 7 - 9) hepatic impairment. In patients with mild and moderate hepatic impairment, phentermine AUC was 37% and 60% higher compared to healthy volunteers. Pharmacokinetics of topiramate was not affected in patients with mild and moderate hepatic impairment when compared with healthy volunteers. QSYMIA has not been studied in patients with severe hepatic impairment (Child-Pugh score 10 - 15) [see Dosage and Administration (2.5)and Use in Specific Populations (8.7)] .

Pediatric Patients 12 to 17 years old

A randomized, double-blind, placebo-controlled study was conducted to evaluate the population pharmacokinetics of QSYMIA using data from 37 pediatric patients (12 to 17 years of age) with obesity. QSYMIA dosages of 3.75 mg/23 mg, 7.5 mg/46 mg, and 15 mg/92 mg were studied. QSYMIA exposure in the pediatric patients appeared comparable to that in adults.

Drug Interaction Studies

In Vitro Assessment of Drug Interactions

Phentermine

Phentermine is not an inhibitor of CYP isozymes CYP1A2, CYP2C9, CYP2C19, CYP2D6, CYP2E1, and CYP3A4, and is not an inhibitor of monoamine oxidases. Phentermine is not an inducer of CYP1A2, CYP2B6, and CYP3A4. Phentermine is not a P-glycoprotein substrate.

Topiramate

Topiramate is not an inhibitor of CYP isozymes CYP1A2, CYP2A6, CYP2B6, CYP2C9, CYP2D6, CYP2E1, and CYP3A4/5. However, topiramate is a mild inhibitor of CYP2C19. Topiramate is a mild inducer of CYP3A4. Topiramate is not a P-glycoprotein substrate.

Effects of Phentermine/Topiramate on Other Drugs

Table 7 describes the effect of phentermine/topiramate on the pharmacokinetics of co-administered drugs.

Table 7. Effect of Phentermine/Topiramate on the Pharmacokinetics of Co-administered Drugs
Phentermine/Topiramate | Co-administered Drug and Dosing Regimen
Phentermine/Topiramate | Drug and Dose (mg) | Change in AUC | Change in Cmax
[A single study examined the effect of multiple-dose QSYMIA 15 mg/92 mg once daily on the pharmacokinetics of multiple-dose 500 mg metformin twice daily and multiple-dose 100 mg sitagliptin once daily in 10 males and 10 females (mean BMI of 27.1 kg/m 2 and range of 22.2 – 32.7 kg/m 2). The study participants received metformin, sitagliptin, phentermine/topiramate only, phentermine/topiramate plus probenecid, phentermine/topiramate plus metformin, and phentermine/topiramate plus sitagliptin on Days 1 – 5, 6 – 10, 11 – 28, 29, 30 – 34, and 35 – 39, respectively. The significance of these interactions is unknown.] 15 mg/92 mg dose QD for 16 days | Metformin 500 mg BID for 5 days | ↑ 23% | ↑ 16%
15 mg/92 mg dose QD for 21 days | Sitagliptin 100 mg QD for 5 days | ↓ 3% | ↓ 9%
[See Drug Interactions (7)] 15 mg/92 mg dose QD for 15 days | Oral contraceptive single dose norethindrone 1 mg ethinyl estradiol 35 mcg | ↑ 16% ↓ 16% | ↑ 22% ↓ 8%

Effect of Other Drugs on Phentermine/Topiramate

Table 8 describes the effect of other drugs on the pharmacokinetics of phentermine/topiramate.

Table 8. Effect of Co-administered Drugs on the Pharmacokinetics of Phentermine/Topiramate
Co-administered Drug and Dosing Regimen | Phentermine/Topiramate
Co-administered Drug and Dosing Regimen | Dose (mg) | Change in AUC | Change in Cmax
Topiramate 92 mg single dose | 15 mg phentermine single dose | ↑ 42% | ↑ 13%
Phentermine 15 mg single dose | 92 mg topiramate single dose | ↑ 6% | ↑ 2%
[The same single study examined the effect of multiple-dose 500 mg metformin twice daily, a single-dose 2 g probenecid, and multiple-dose 100 mg sitagliptin once daily on the pharmacokinetics of multiple-dose phentermine/topiramate 15 mg/92 mg once daily in 10 males and 10 females (mean BMI of 27.1 kg/m 2 and range of 22.2 – 32.7 kg/m 2). The study participants received metformin, sitagliptin, phentermine/topiramate only, phentermine/topiramate plus probenecid, phentermine/topiramate plus metformin, and phentermine/topiramate plus sitagliptin on Days 1 – 5, 6 – 10, 11 – 28, 29, 30 – 34, and 35 – 39, respectively.] Metformin 500 mg BID for 5 days | 15 mg/92 mg dose QD for 16 days phentermine topiramate | ↑ 5% ↓ 5% | ↑ 7% ↓ 4%
Sitagliptin 100 mg QD for 5 days | 15 mg/92 mg dose QD for 21 days phentermine topiramate | ↑ 9% ↓ 2% | ↑ 10% ↓ 2%
Probenecid 2 g QD | 15 mg/92 mg dose QD for 11 days phentermine topiramate | ↓ 0.3% ↑ 0.7% | ↑ 4% ↑ 3%

Effects of Topiramate Alone on Other Drugs and Effects of Other Drugs on Topiramate

Antiepileptic Drugs

Potential interactions between topiramate and standard antiepileptic (AED) drugs were assessed in controlled clinical pharmacokinetic studies in patients with epilepsy. The effects of these interactions on mean plasma AUCs are summarized in Table 9.

In Table 9, the second column (AED concentration) describes what happens to the concentration of the AED listed in the first column when topiramate is added. The third column (topiramate concentration) describes how the co-administration of a drug listed in the first column modifies the concentration of topiramate in experimental settings when topiramate was given alone [see Drug Interactions (7)] .

Table 9. Summary of AED Interactions with Topiramate
AED Co-administered | AED Concentration | Topiramate Concentration
NC = Less than 10% change in plasma concentration; NE = Not Evaluated; TPM = topiramate
Phenytoin | NC or 25% increase [Plasma concentration increased 25% in some patients, generally those on a twice a day dosing regimen of phenytoin.] | 48% decrease
Carbamazepine (CBZ) | NC | 40% decrease
CBZ epoxide [Is not administered but is an active metabolite of carbamazepine.] | NC | NE
Valproic acid | 11% decrease | 14% decrease
Phenobarbital | NC | NE
Primidone | NC | NE
Lamotrigine | NC at TPM doses up to 400 mg/day | 13% decrease

Digoxin

In a single-dose study, serum digoxin AUC was decreased by 12% with concomitant topiramate administration. The clinical relevance of this observation has not been established.

Hydrochlorothiazide

A drug-drug interaction study conducted in healthy volunteers evaluated the steady-state pharmacokinetics of hydrochlorothiazide (HCTZ) (25 mg q24h) and topiramate (96 mg q12h) when administered alone and concomitantly. The results of this study indicate that topiramate Cmax increased by 27% and AUC increased by 29% when HCTZ was added to topiramate. The clinical significance of this change is unknown. The steady-state pharmacokinetics of HCTZ were not significantly influenced by the concomitant administration of topiramate. Clinical laboratory results indicated decreases in serum potassium after topiramate or HCTZ administration, which were greater when HCTZ and topiramate were administered in combination [see Drug Interactions (7) and Warnings and Precautions (5.12)] .

Pioglitazone

A drug-drug interaction study conducted in healthy volunteers evaluated the steady-state pharmacokinetics of topiramate (96 mg twice daily) and pioglitazone (30 mg daily) when administered alone and concomitantly for 7 days. A 15% decrease in the area under the concentration-time curve during a dosage interval at steady state (AUCτ,ss) of pioglitazone with no alteration in maximum steady-state plasma drug concentration during a dosage interval (Cmax,ss) was observed. This finding was not statistically significant. In addition, a 13% and 16% decrease in Cmax,ss and AUCτ,ss respectively, of the active hydroxy-metabolite was noted as well as a 60% decrease in Cmax,ss and AUCτ,ss of the active keto-metabolite [see Drug Interactions (7)] .

Glyburide

A drug-drug interaction study conducted in patients with type 2 diabetes mellitus evaluated the steady-state pharmacokinetics of glyburide (5 mg/day) alone and concomitantly with topiramate (150 mg/day). There was a 22% decrease in Cmax and a 25% reduction in AUC24 for glyburide during topiramate administration. Systemic exposure (AUC) of the active metabolites, 4- trans-hydroxyglyburide (M1), and 3- cis-hydroxyglyburide (M2), was reduced by 13% and 15%, and Cmax was reduced by 18% and 25%, respectively. The steady-state pharmacokinetics of topiramate were unaffected by concomitant administration of glyburide.

Lithium

In patients, the pharmacokinetics of lithium were unaffected during treatment with topiramate at doses of 200 mg/day; however, there was an observed increase in systemic exposure of lithium (27% for Cmax and 26% for AUC) following topiramate doses up to 600 mg/day.

Haloperidol

The pharmacokinetics of a single dose of haloperidol (5 mg) were not affected following multiple dosing of topiramate (100 mg every 12 hours) in 13 healthy adults (6 males, 7 females).

Amitriptyline

There was a 12% increase in AUC and Cmax for amitriptyline (25 mg per day) in 18 normal subjects (9 males, 9 females) receiving 200 mg/day of topiramate [see Drug Interactions (7)] .

Sumatriptan

Multiple dosing of topiramate (100 mg every 12 hrs) in 24 healthy volunteers (14 males, 10 females) did not affect the pharmacokinetics of single-dose sumatriptan either orally (100 mg) or subcutaneously (6 mg).

Risperidone

When administered concomitantly with topiramate at escalating doses of 100, 250, and 400 mg/day, there was a reduction in risperidone systemic exposure (16% and 33% for steady-state AUC at the 250 and 400 mg/day doses of topiramate). No alterations of 9-hydroxyrisperidone levels were observed. Co-administration of topiramate 400 mg/day with risperidone resulted in a 14% increase in Cmax and a 12% increase in AUC12 of topiramate. There were no clinically significant changes in the systemic exposure of risperidone plus 9-hydroxyrisperidone or of topiramate; therefore, this interaction is not likely to be of clinical significance.

Propranolol

Multiple dosing of topiramate (200 mg/day) in 34 healthy volunteers (17 males, 17 females) did not affect the pharmacokinetics of propranolol following daily 160 mg doses. Propranolol doses of 160 mg/day in 39 volunteers (27 males, 12 females) had no effect on the exposure to topiramate, at a dose of 200 mg/day of topiramate.

Dihydroergotamine

Multiple dosing of topiramate (200 mg/day) in 24 healthy volunteers (12 males, 12 females) did not affect the pharmacokinetics of a 1 mg subcutaneous dose of dihydroergotamine. Similarly, a 1 mg subcutaneous dose of dihydroergotamine did not affect the pharmacokinetics of a 200 mg/day dose of topiramate in the same study.

Diltiazem

Co-administration of diltiazem hydrochloride extended-release with topiramate (150 mg/day) resulted in a 10% decrease in Cmax and a 25% decrease in diltiazem AUC, a 27% decrease in Cmax and an 18% decrease in des-acetyl diltiazem AUC, and no effect on N-desmethyl diltiazem. Co-administration of topiramate with diltiazem hydrochloride extended-release resulted in a 16% increase in Cmaxand a 19% increase in AUC12 of topiramate.

Venlafaxine

Multiple dosing of topiramate (150 mg/day) in healthy volunteers did not affect the pharmacokinetics of venlafaxine or O-desmethyl venlafaxine. Multiple dosing of venlafaxine (150 mg extended release) did not affect the pharmacokinetics of topiramate.

13 NONCLINICAL TOXICOLOGY

13.1 Carcinogenesis, Mutagenesis, Impairment of Fertility

Phentermine/Topiramate

No animal studies have been conducted with the combination of phentermine/topiramate to evaluate carcinogenesis, mutagenesis, or impairment of fertility. The following data are based on findings in studies performed individually with phentermine or topiramate, QSYMIA's two active ingredients.

Phentermine

Phentermine was not mutagenic or clastogenic with or without metabolic activation in the Ames bacterial mutagenicity assay, a chromosomal aberration test in Chinese hamster lung (CHL-K1) cells, or an in vivo micronucleus assay.

Rats were administered oral doses of 3, 10, and 30 mg/kg/day phentermine for 2 years. There was no evidence of carcinogenicity at the highest dose of phentermine (30 mg/kg) which is approximately 11 to 15 times the maximum recommended clinical dose of QSYMIA 15 mg/92 mg based on AUC exposure.

No animal studies have been conducted with phentermine to determine the potential for impairment of fertility.

Topiramate

Topiramate did not demonstrate genotoxic potential when tested in a battery of in vitro and in vivo assays. Topiramate was not mutagenic in the Ames test or the in vitro mouse lymphoma assay; it did not increase unscheduled DNA synthesis in rat hepatocytes in vitro; and it did not increase chromosomal aberrations in human lymphocytes in vitro or in rat bone marrow in vivo.

An increase in urinary bladder tumors was observed in mice given topiramate (20, 75, and 300 mg/kg) in the diet for 21 months. The elevated bladder tumor incidence, which was statistically significant in males and females receiving 300 mg/kg, was primarily due to the increased occurrence of a smooth muscle tumor considered histomorphologically unique to mice. Plasma exposures in mice receiving 300 mg/kg were approximately 2 to 4 times steady-state exposures measured in patients receiving topiramate monotherapy at the MRHD of QSYMIA 15 mg/92 mg. The relevance of this finding to human carcinogenic risk is uncertain. No evidence of carcinogenicity was seen in rats following oral administration of topiramate for 2 years at doses up to 120 mg/kg (approximately 4 to 10 times the MRHD of QSYMIA based on AUC estimates).

No adverse effects on male or female fertility were observed in rats at doses up to 100 mg/kg (approximately 4 to 8 times male and female MRHD exposures of QSYMIA based on AUC).

14 CLINICAL STUDIES

Clinical Studies in Adults

The effect of QSYMIA on weight loss in conjunction with reduced caloric intake and increased physical activity was studied in two randomized, double-blind, placebo-controlled studies in patients with obesity (Study 1) and patients with obesity or overweight with two or more significant co-morbidities (Study 2). Both studies had a 4-week titration period, followed by 52 weeks of treatment. There were two co-primary efficacy outcomes measured after 1 year of treatment (Week 56): 1) the percent weight loss from baseline; and 2) treatment response defined as achieving at least 5% weight loss from baseline.

In Study 1 (NCT00554216), patients with obesity (BMI greater than or equal to 35 kg/m^2) were randomized to receive 1 year of treatment with placebo (N=514), QSYMIA 3.75 mg/23 mg (N=241), or QSYMIA 15 mg/ 92 mg (N=512) in a 2:1:2 ratio. Patients ranged in age from 18-71 years old (mean age 43) and 83% were female. Approximately 80% were White, 18% were Black or African American, and 15% were Hispanic or Latino ethnicity. At the beginning of the study the average weight and BMI of patients was 116 kg and 42 kg/m^2, respectively. Patients with type 2 diabetes mellitus were excluded from participating in Study 1. During the study, a well-balanced, reduced-calorie diet to result in an approximate 500 kcal/day decrease in caloric intake was recommended to all patients and patients were offered nutritional and lifestyle modification counseling.

In Study 2 (NCT00553787), patients with overweight or obesity were randomized to receive 1 year of treatment with placebo (N=994), QSYMIA 7.5 mg/46 mg (N=498), or QSYMIA 15 mg/92 mg (N=995) in a 2:1:2 ratio. Eligible patients had to have a BMI greater than or equal to 27 kg/m^2 and less than or equal to 45 kg/m^2 (there was no lower limit on BMI for patients with type 2 diabetes mellitus) and two or more of the following obesity-related co-morbid conditions:

- Elevated blood pressure (greater than or equal to 140/90 mmHg, or greater than or equal to 130/85 mmHg for diabetics) or requirement for greater than or equal to 2 antihypertensive medications;
- Triglycerides greater than 200-400 mg/dL or were receiving treatment with 2 or more lipid-lowering agents;
- Elevated fasting blood glucose (greater than 100 mg/dL) or diabetes; and/or
- Waist circumference greater than or equal to 102 cm for men or greater than or equal to 88 cm for females.

Patients ranged in age from 19 to71 years of age (mean age 51) and 70% were female. Approximately 86% were White, 12% were Black or African American, and 13% were Hispanic or Latino ethnicity. The average weight and BMI of patients at the start of the study was 103 kg and 36.6 kg/m^2, respectively. Approximately half (53%) of patients had hypertension at the start of the study. There were 388 (16%) patients with type 2 diabetes mellitus at the start of the study. During the study, a well-balanced, reduced-calorie diet to result in an approximate 500 kcal/day decrease in caloric intake was recommended to all patients and patients were offered nutritional and lifestyle modification counseling.

The percentage of randomized patients who withdrew from each study prior to week 56 was 40% in Study 1, and 31% in Study 2.

Table 10 provides the results for weight loss at 1 year in Studies 1 and 2. After 1 year of treatment with QSYMIA, all dose levels resulted in statistically significant weight loss compared to placebo (see Table 10, Figure 1 and Figure 2). A statistically significant greater proportion of the patients randomized to QSYMIA than placebo achieved 5% and 10% weight loss.

Table 10. Weight Loss at One Year in Adult Patients in Studies 1 and 2
Analysis Method | Study 1 (Obesity) |  |  | Study 2 (Obesity or Overweight with Co-morbidities)
Analysis Method | Placebo | QSYMIA 3.75 mg/23 mg | QSYMIA 15 mg/92 mg | Placebo | QSYMIA 7.5 mg/46 mg | QSYMIA 15 mg/92 mg
SD=standard deviation; LS=least-squares; SE=standard error; CI=confidence interval
Type 1 error was controlled across all pairwise treatment comparisons.
ITT-LOCF (Primary) [Uses all available data from subjects in ITT population, including data collected from subjects who discontinued drug but remained on study. Last Observation Carried Forward (LOCF) method used to impute missing data.] | n = 498 | n = 234 | n = 498 | n = 979 | n = 488 | n = 981
Weight (kg)
Baseline mean (SD) | 115.7 (21.4) | 118.6 (21.9) | 115.2 (20.8) | 103.3 (18.1) | 102.8 (18.2) | 103.1 (17.6)
% LS Mean Change from baseline (SE) [Adjusted for baseline bodyweight (Study 1) and baseline bodyweight and diabetic status (Study 2).] | -1.6 (0.4) | -5.1 (0.5) [p < 0.0001 vs. placebo based on least-squares (LS) mean from an analysis of covariance.] | -10.9 (0.4) [p < 0.01 vs. 3.75 mg/23 mg (Study 1) or 7.5 mg/46 mg (Study 2) dose.] | -1.2 (0.3) | -7.8 (0.4) | -9.8 (0.3)
Difference from placebo (95% CI) |  | 3.5 (2.4-4.7) | 9.4 (8.4-10.3) |  | 6.6 (5.8-7.4) | 8.6 (8.0-9.3)
Percentage of patients losing greater than or equal to 5% body weight | 17% | 45% | 67% | 21% | 62% | 70%
Risk Difference vs. placebo (95% CI) |  | 27.6 (20.4-34.8) | 49.4 (44.1-54.7) |  | 41.3 (36.3-46.3) | 49.2 (45.4-53.0)
Percentage of patients losing greater than or equal to 10% body weight | 7% | 19% | 47% | 7% | 37% | 48%
Risk Difference vs. placebo (95% CI) |  | 11.4 (5.9-16.9) | 39.8 (34.8-44.7) |  | 29.9 (25.3-34.5) | 40.3 (36.7-43.8)

Figure 1.

Study 1 Percent Weight Change from Baseline to Week 56 in Adults with Obesity

Figure 2.

Study 2 Percent Weight Change from Baseline to Week 56 in Adults with Obesity or Overweight with Co-morbidities

p<0.0001 for all three Qsymia doses vs placebo, and 15 mg/92 mg vs 7.5 mg/46 mg or 3.75 mg/23 mg at all time points for both completers and ITT-LOCF

The changes in cardiovascular, metabolic, and anthropometric risk factors associated with obesity from Study 1 and 2 are presented in Table 11 and Table 12.

Table 11. Least-Squares (LS) Mean [Study 1 adjusted for baseline bodyweight] Change from Baseline and Treatment Difference from Placebo in Cardiometabolic Parameters in Adults Following One Year of Treatment in Study 1 (Obesity)
Study 1 (Obesity) | Placebo (N=498) | QSYMIA 3.75 mg/23 mg (N=234) | QSYMIA 15 mg/92 mg (N=498) | QSYMIA – Placebo: LS Mean
Study 1 (Obesity) | Placebo (N=498) | QSYMIA 3.75 mg/23 mg (N=234) | QSYMIA 15 mg/92 mg (N=498) | QSYMIA 3.75 mg/23 mg | QSYMIA 15 mg/92 mg
SD=standard deviation; SE=standard error
Heart Rate, bpm
Baseline mean (SD) | 73.2 (8.8) | 72.3 (9.2) | 73.1 (9.6) | +1.1 | +1.8
LS Mean Change (SE) | -0.8 (0.5) | +0.3 (0.6) | +1.0 (0.5) | +1.1 | +1.8
Systolic Blood Pressure, mmHg
Baseline mean (SD) | 121.9 (11.5) | 122.5 (11.1) | 121.9 (11.6) | -2.8 | -3.8
LS Mean Change (SE) | +0.9 (0.6) | -1.8 (0.8) | -2.9 (0.6) | -2.8 | -3.8
Diastolic Blood Pressure, mmHg
Baseline mean (SD) | 77.2 (7.9) | 77.8 (7.5) | 77.4 (7.7) | -0.5 | -1.9
LS Mean Change (SE) | +0.4 (0.4) | -0.1 (0.6) | -1.5 (0.4) | -0.5 | -1.9
Total Cholesterol, %
Baseline mean (SD) | 194.3 (36.7) | 196.3 (36.5) | 192.7 (33.8) | -1.9 | -2.5
LS Mean Change (SE) | -3.5 (0.6) | -5.4 (0.9) | -6.0 (0.6) | -1.9 | -2.5
LDL-Cholesterol, %
Baseline mean (SD) | 120.9 (32.2) | 122.8 (33.4) | 120.0 (30.1) | -2.2 | -2.8
LS Mean Change (SE) | -5.5 (1.0) | -7.7 (1.3) | -8.4 (0.9) | -2.2 | -2.8
HDL-Cholesterol, %
Baseline mean (SD) | 49.5 (13.3) | 50.0 (11.1) | 49.7 (11.7) | +0.5 | +3.5
LS Mean Change (SE) | +0.0 (0.8) | +0.5 (1.1) | +3.5 (0.8) | +0.5 | +3.5
Triglycerides, %
Baseline mean (SD) | 119.0 (39.3) | 117.5 (40.3) | 114.6 (37.1) | -3.9 | -14.3
LS Mean Change (SE) | +9.1 (2.3) | +5.2 (3.1) | -5.2 (2.2) | -3.9 | -14.3
Fasting Glucose, mg/dL
Baseline mean (SD) | 93.1 (8.7) | 93.9 (9.2) | 93.0 (9.5) | -1.2 | -2.5
LS Mean Change (SE) | +1.9 (0.5) | +0.8 (0.7) | -0.6 (0.5) | -1.2 | -2.5
Waist Circumference, cm
Baseline mean (SD) | 120.5 (14.0) | 121.5 (15.2) | 120.0 (14.7) | -2.5 [Statistically significant versus placebo based on the pre-specified method for controlling Type I error across multiple doses] | -7.8
LS Mean Change (SE) | -3.1 (0.5) | -5.6 (0.6) | -10.9 (0.5) | -2.5 [Statistically significant versus placebo based on the pre-specified method for controlling Type I error across multiple doses] | -7.8

Table 12. Least-Squares (LS) Mean [Study 2 adjusted for baseline bodyweight and diabetic status] Change from Baseline and Treatment Difference from Placebo in Cardiometabolic Parameters in Adults Following One Year of Treatment in Study 2 (Obese or Overweight with Comorbidities)
Study 2 (Overweight and Obese with Comorbidities) | Placebo (N=979) | QSYMIA 7.5 mg/46 mg (N=488) | QSYMIA 15 mg/92 mg (N=981) | QSYMIA – Placebo: LS Mean
Study 2 (Overweight and Obese with Comorbidities) | Placebo (N=979) | QSYMIA 7.5 mg/46 mg (N=488) | QSYMIA 15 mg/92 mg (N=981) | QSYMIA 7.5 mg/46 mg | QSYMIA 15 mg/92 mg
SD=standard deviation; SE=standard error
Heart Rate, bpm
Baseline mean (SD) | 72.1 (9.9) | 72.2 (10.1) | 72.6 (10.1) | +0.6 | +1.7
LS Mean Change (SE) | -0.3 (0.3) | +0.3 (0.4) | +1.4 (0.3) | +0.6 | +1.7
Systolic Blood Pressure, mmHg
Baseline mean (SD) | 128.9 (13.5) | 128.5 (13.6) | 127.9 (13.4) | -2.3 | -3.2
LS Mean Change (SE) | -2.4 (0.48) | -4.7 (0.63) | -5.6 (0.5) | -2.3 | -3.2
Diastolic Blood Pressure, mmHg
Baseline mean (SD) | 81.1 (9.2) | 80.6 (8.7) | 80.2 (9.1) | -0.7 | -1.1
LS Mean Change (SE) | -2.7 (0.3) | -3.4 (0.4) | -3.8 (0.3) | -0.7 | -1.1
Total Cholesterol, %
Baseline mean (SD) | 205.8 (41.7) | 201.0 (37.9) | 205.4 (40.4) | -1.6 | -3.0
LS Mean Change (SE) | -3.3 (0.5) | -4.9 (0.7) | -6.3 (0.5) | -1.6 | -3.0
LDL-Cholesterol, %
Baseline mean (SD) | 124.2 (36.2) | 120.3 (33.7) | 123.9 (35.6) | +0.4 | -2.8
LS Mean Change (SE) | -4.1 (0.9) | -3.7 (1.1) | -6.9 (0.9) | +0.4 | -2.8
HDL-Cholesterol, %
Baseline mean (SD) | 48.9 (13.8) | 48.5 (12.8) | 49.1 (13.8) | +4.0 | +5.6
LS Mean Change (SE) | +1.2 (0.7) | +5.2 (0.9) | +6.8 (0.7) | +4.0 | +5.6
Triglycerides, %
Baseline mean (SD) | 163.5 (76.3) | 161.1 (72.2) | 161.9 (73.4) | -13.3 | -15.3
LS Mean Change (SE) | +4.7 (1.7) | -8.6 (2.2) | -10.6 (1.7) | -13.3 | -15.3
Fasting Insulin, (µIU/mL)
Baseline mean (SD) | 17.8 (13.2) | 18.0 (12.9) | 18.4 (17.5) | -4.2 | -4.7
LS Mean Change (SE) | +0.7 (0.8) | -3.5 (1.1) | -4.0 (0.8) | -4.2 | -4.7
Fasting Glucose, mg/dL
Baseline mean (SD) | 106.6 (23.7) | 106.2 (21.0) | 105.7 (21.4) | -2.4 | -3.6
LS Mean Change (SE) | +2.3 (0.6) | -0.1 (0.8) | -1.3 (0.6) | -2.4 | -3.6
Waist Circumference, cm
Baseline mean (SD) | 113.4 (12.2) | 112.7 (12.4) | 113.2 (12.2) | -5.2 [Statistically significant versus placebo based on the pre-specified method for controlling Type I error across multiple doses] | -6.8
LS Mean Change (SE) | -2.4 (0.3) | -7.6 (0.4) | -9.2 (0.3) | -5.2 [Statistically significant versus placebo based on the pre-specified method for controlling Type I error across multiple doses] | -6.8

Among the 388 subjects with type 2 diabetes mellitus treated in Study 2, reductions in HbA1c from baseline (6.8%) were 0.1% for placebo compared to 0.4% and 0.4% with QSYMIA 7.5 mg/46 mg and QSYMIA 15 mg/92 mg, respectively.

Clinical Studies in Pediatric Patients Aged 12 Years and Older

The effect of QSYMIA on BMI in conjunction with reduced caloric intake and increased physical activity was evaluated in Study 3 (NCT03922945), a 56-week, randomized, double-blind, placebo-controlled study in pediatric patients (12 to 17 years of age) with BMI ≥ 95th percentile standardized by age and sex. Patients were randomized to receive treatment with placebo (N=56), QSYMIA 7.5 mg/46 mg (N=54), or QSYMIA 15 mg/ 92 mg (N=113) in a 1:1:2 ratio. During the study, a well-balanced, reduced-calorie diet to result in an approximate 500 kcal/day decrease in caloric intake was recommended to all patients and patients were offered a family-based lifestyle modification program for adolescents.

Patients' mean age was 14 years old, approximately 55% were female, 67% were White, 26% were Black or African American, and 33% were Hispanic or Latino ethnicity. At the beginning of the study, the average weight and BMI of patients was 106 kg and 38 kg/m^2, respectively, with approximately 81% considered severely obese (120% of the 95th percentile or greater for BMI standardized by age and sex). Thirty-eight (38%) of randomized patients withdrew from the study prior to week 56.

The primary efficacy parameter was mean percent change in BMI. Table 13 provides results for BMI reduction at Week 56 in Study 3. After 56 weeks of treatment with QSYMIA, all dose levels resulted in statistically significant reduction in BMI compared to placebo (see Table 13, Figure 3). A greater proportion of patients randomized to QSYMIA than placebo achieved 5%, 10%, and 15% BMI reduction.

Table 13. Change in BMI at Week 56 in Pediatric Patients Aged 12 to 17 Years in Study 3 (Obesity)
Analysis Method | Placebo | QSYMIA 7.5 mg/46 mg | QSYMIA 15 mg/92 mg
SD=standard deviation; LS=least-squares; SE=standard error; CI=confidence interval
ITT-Washout (Primary) [Missing data were imputed using a washout multiple imputation method based on placebo response.] | n = 56 | n = 54 | n = 113
BMI (kg/m^2) Primary Efficacy Endpoint
Baseline mean (SD) | 36.4 (6.4) | 36.9 (6.7) | 39.0 (7.4)
% LS Mean Change from baseline (SE) | +3.3 (1.4) | -4.8 (1.3) | -7.1 (1.0)
Difference from placebo (95% CI) |  | -8.1 (-11.9, -4.3) | -10.4 (-13.9, -7.0)
Percentage of patients with a reduction of greater than or equal to 5% BMI | 13.6% | 44.0% | 52.2%
Difference vs. placebo (95% CI) |  | 29.7% (11.2, 48.3) | 38.6% (23.1, 54.1)
Percentage of patients with a reduction of greater than or equal to 10% BMI | 4.5% | 33.5% | 44.4%
Difference vs. placebo (95% CI) |  | 28.8% (13.6, 44.0) | 40.5% (28.4, 52.6)
Percentage of patients with a reduction of greater than or equal to 15% BMI | 2.9% | 13.6% | 28.9%
Difference vs. placebo (95% CI) |  | 11.7% (1.3, 22.2) | 27.4% (17.7, 37.1)

Figure 3. Study 3 Percent BMI Change from Baseline to Week 56 in Pediatric Patients Aged 12 to 17 Years with Obesity

The changes in cardiovascular, metabolic, and anthropometric risk factors associated with obesity from Study 3 are presented in Table 14.

Table 14. Change from Baseline and Treatment Difference from Placebo in Cardiometabolic Parameters in Pediatric Patients Aged 12 to 17 Years Following 56 Weeks of Treatment in Study 3 (Obesity)
Study 3 (Obesity) ITT Population | Placebo (N=56) | QSYMIA 7.5 mg/46 mg (N=54) | QSYMIA 15 mg/92 mg (N=113) | QSYMIA – Placebo
Study 3 (Obesity) ITT Population | Placebo (N=56) | QSYMIA 7.5 mg/46 mg (N=54) | QSYMIA 15 mg/92 mg (N=113) | QSYMIA 7.5 mg/46 mg | QSYMIA 15 mg/92 mg
SD=standard deviation; SE=standard error
Heart Rate, bpm [Parameter was not pre-specified for inferential statistics; descriptive summary of change from baseline provided for subjects with non-missing data at baseline and Week 56.]
Baseline mean (SD) | 76.8 (9.9) | 78.6 (9.6) | 76.2 (9.6) | -5.6 | 3.2
Mean Change (SD) | 2.5 (12.4) | -3.1 (8.4) | 5.7 (11.4) | -5.6 | 3.2
Systolic Blood Pressure, mmHg
Baseline mean (SD) | 117.7 (10.4) | 121.4 (9.2) | 117.4 (10.2) | -2.8 | -1.0
LS Mean Change (SE) | +2.9 (1.6) | +0.1 (1.5) | +1.8 (1.1) | -2.8 | -1.0
Diastolic Blood Pressure, mmHg
Baseline mean (SD) | 71.7 (8.3) | 75.8 (6.7) | 72.9 (7.3) | -3.2 | -2.2
LS Mean Change (SE) | +3.4 (1.5) | +0.2 (1.3) | +1.2 (1.0) | -3.2 | -2.2
Total Cholesterol, mg/dL
Baseline mean (SD) | 164.9 (30.9) | 160.6 (26.1) | 159.4 (32.7) | -1.4 | -1.2
Mean % Change (SD) | -1.8 (10.7) | -3.2 (13.1) | -3.0 (14.5) | -1.4 | -1.2
LDL-Cholesterol, mg/dL
Baseline mean (SD) | 94.1 (26.8) | 89.4 (23.7) | 90.2 (27.3) | -3.9 | -2.5
Mean % Change (SD) | 0.2 (23.3) | -3.7 (15.5) | -2.3 (21.6) | -3.9 | -2.5
HDL-Cholesterol, mg/dL
Baseline mean (SD) | 47.2 (9.7) | 47.2 (8.9) | 46.7 (10.1) | 6.4 | 5.0
LS Mean % Change (SE) | -4.3 (15.1) | +2.1 (11.5) | +0.7 (9.6) | 6.4 | 5.0
Triglycerides, mg/dL
Baseline mean (SD) | 118.3 (46.1) | 120.1 (61.6) | 112.2 (63.2) | -11.7 | -11.2
LS Mean % Change (SE) | +5.6 (8.4) | -6.2 (8.0) | -5.6 (7.2) | -11.7 | -11.2
HbA1c, %
Baseline mean (SD) | 5.5 (0.3) | 5.6 (0.4) | 5.5 (0.4) | -0.2 | 0.0
Mean Change (SD) | -0.2 (0.2) | -0.4 (0.3) | -0.2 (0.3) | -0.2 | 0.0
Waist Circumference, cm
Baseline mean (SD) | 111.1 (14.0) | 111.9 (15.5) | 116.5 (16.8) | -5.6 | -7.6
LS Mean Change (SE) | +0.6 (1.4) | -5.0 (1.4) | -7.0 (1.1) | -5.6 | -7.6

16 HOW SUPPLIED/STORAGE AND HANDLING

QSYMIA (phentermine and topiramate extended-release capsules) are available as follows (see Table 15):

Table 15. QSYMIA Presentations
Strength (phentermine mg/topiramate mg) | Description | How Supplied | NDC
3.75 mg/23 mg extended-release capsules | Purple cap imprinted with VIVUS, Purple body imprinted with 3.75/23 | Unit of Use Bottle (14 capsules) | 62541-201-14
3.75 mg/23 mg extended-release capsules | Purple cap imprinted with VIVUS, Purple body imprinted with 3.75/23 | Pharmacy Bottle (30 capsules) | 62541-201-30
7.5 mg/46 mg extended-release capsules | Purple cap imprinted with VIVUS, Yellow body imprinted with 7.5/46 | Unit of Use Bottle (30 capsules) | 62541-202-30
11.25 mg/69 mg extended-release capsules | Yellow cap imprinted with VIVUS, Yellow body imprinted with 11.25/69 | Pharmacy Bottle (30 capsules) | 62541-203-30
15 mg/92 mg extended-release capsules | Yellow cap imprinted with VIVUS, White body imprinted with 15/92 | Unit of Use Bottle (30 capsules) | 62541-204-30
3.75 mg/23 mg and 7.5 mg/46 mg extended-release capsules | Purple cap imprinted with VIVUS, Purple body imprinted with 3.75/23 and Purple cap imprinted with VIVUS, Yellow body imprinted with 7.5/46 | Starter Pack - Blister Configuration (28 Capsules) | 62541-210-28
11.25 mg/69 mg and 15 mg/92 mg extended-release capsules | Yellow cap imprinted with VIVUS, Yellow body imprinted with 11.25/69 | Dose Escalation Pack – Blister Configuration (28 Capsules) | 62541-220-28

STORAGE AND HANDLING

Store at 20°C to 25°C (68°F to 77°F), excursions permitted between 15°C and 30°C (59°F and 86°F) [see USP Controlled Room Temperature]. Keep container tightly closed and protect from moisture.

17 PATIENT COUNSELING INFORMATION

Advise the patient to read the FDA-approved patient labeling (Medication Guide).

Embryo-Fetal Toxicity

Inform patients who can become pregnant that QSYMIA can cause fetal harm and patients should avoid getting pregnant while taking QSYMIA [see Warnings and Precautions (5.1), Drug Interactions (7), and Use in Specific Populations (8.3)] .

Advise patients who can become pregnant:

- that pregnancy testing is recommended before initiating QSYMIA and monthly during therapy;
- to use effective contraception during QSYMIA therapy;
- who experience spotting while taking a combined oral contraceptive to notify their health care provider;
- with a known or suspected pregnancy to stop QSYMIA immediately and notify their health care provider.

Access to QSYMIA

Advise patients that QSYMIA is only available through certified pharmacies that are enrolled in the QSYMIA certified pharmacy network. Advise patients on how to access QSYMIA through certified pharmacies. Additional information may be obtained via the website www.QSYMIAREMS.com or by telephone at 1-888-998-4887.

Suicidal Behavior and Ideation and Mood and Sleep Disorders

Inform patients that QSYMIA can increase the risk of mood changes, sleep disorders, depression, and suicidal ideation. Advise patients to tell their health care provider(s) immediately if mood changes, depression, or suicidal ideation occur [see Warnings and Precautions (5.2, 5.4)] .

Ophthalmologic Adverse Reactions

Inform patients that QSYMIA can increase the risk of acute myopia, secondary angle closure glaucoma, and visual field defects. Advise patients to immediately report symptoms of severe and persistent eye pain or significant changes in their vision to their health care provider(s) [see Warnings and Precautions (5.3)].

Cognitive Impairment

Inform patients that QSYMIA can cause confusion, concentration, and word-finding difficulties. Inform patients that the concomitant use of alcohol or central nervous system (CNS) depressant drugs with QSYMIA, may increase the risk of dizziness, cognitive adverse reactions, drowsiness, light-headedness, impaired coordination and somnolence.

Advise patients to tell their health care provider(s) about any changes in attention, concentration, memory, difficulty finding words, or other cognitive functions.

Advise patients not to drive or operate machinery until they have gained sufficient experience on QSYMIA to gauge whether it adversely affects their mental performance, motor performance, and/or vision. Advise patients to avoid excessive alcohol intake while taking QSYMIA [see Warnings and Precautions (5.5)] .

Slowing of Linear Growth

Discuss with the patient and caregiver that long-term QSYMIA treatment may attenuate growth as reflected by slower height increase in pediatric patients [see Warnings and Precautions (5.6)] .

Metabolic Acidosis

Inform patients that QSYMIA can increase the risk of metabolic acidosis. Advise patients to tell their health care provider(s) about any factors that can increase the risk of acidosis (e.g. prolonged diarrhea, surgery, and high protein/low carbohydrate diet, and/or concomitant medications such as carbonic anhydrase inhibitors) [see Warnings and Precautions (5.7)] .

Risk of Seizures with Abrupt Withdrawal of QSYMIA

Inform patients that abrupt withdrawal of topiramate has been associated with seizures in individuals without a history of seizures or epilepsy. Advise patients not to abruptly stop QSYMIA without first talking to their health care provider(s) [see Dosage and Administration (2.3) and Warnings and Precautions (5.9)] .

Kidney Stones

Inform patients that use of QSYMIA has been associated with kidney stone formation. Advise patients to increase fluid intake to increase urinary output which can decrease the concentration of substances involved in kidney stone formation. Advise patients to report symptoms of severe side or back pain, and/or blood in their urine to their health care provider(s) [see Warnings and Precautions (5.10) and Adverse Reactions (6.1)] .

Oligohidrosis and Hyperthermia

Inform patients that oligohidrosis (decreased sweating) has been reported in association with the use of topiramate particularly in pediatric patients. Advise patients to monitor for decreased sweating and increased body temperature during physical activity, especially in hot weather [see Warnings and Precautions (5.11)] .

Serious Skin Reactions

Inform patients that serious skin reactions have been reported with use of topiramate. Inform patients of the signs of serious skin reactions and advise patients to report signs of a skin reaction to their health care provider(s) [see Warnings and Precautions (5.13)] .

Lactation

Advise patients that breastfeeding is not recommended during QSYMIA treatment [see Use in Specific Populations (8.2)] .

Allergic Reactions Due to Inactive Ingredient FD&C Yellow No. 5

Inform patients that this product contains FD&C Yellow No. 5 (tartrazine) which may cause allergic-type reactions (including bronchial asthma) in certain susceptible persons [see Warnings and Precautions (5.14)] .

How to Take QSYMIA

Instruct patients on the dosage titration schedule of QSYMIA. Advise patients to take QSYMIA in the morning with or without food [see Dosage and Administration (2.2)] .

Manufactured for VIVUS LLC by Catalent Pharma Solutions, LLC
1100 Enterprise Drive
Winchester, KY 40391

Copyright © 2012 - 2025 VIVUS LLC All rights reserved.

VIVUS LLC
900 E. Hamilton Ave., Suite 550
Campbell, CA 95008 USA

US Patent Numbers: 7,056,890; 7,553,818; 7,659,256; 7,674,776; 8,580,298; 8,580,299; 8,895,057; 8,895,058, 9,011,905; and 9,011,906
QSYMIA IS A REGISTERED TRADEMARK OF VIVUS LLC

MEDICATION GUIDE
QSYMIA®(Kyoo sim ee uh)
(phentermine and topiramate extended-release capsules)
for oral use, CIV

What is the most important information I should know about QSYMIA?
QSYMIA can cause serious side effects, including :

- Birth defects. If you take QSYMIA during pregnancy, your baby has a higher risk for birth defects including cleft lip and cleft palate. Your baby may also be smaller than expected at birth. The long-term effects of this are not known. These defects can begin early in pregnancy, even before you know you are pregnant.
  Patients who are pregnant must not take QSYMIA.
  Patients who can become pregnant should:
  1. Have a pregnancy test before taking QSYMIA and every month while taking QSYMIA.
  2. Use effective birth control (contraception) consistently while taking QSYMIA. Talk to your health care provider about how to prevent pregnancy.
  If you become pregnant while taking QSYMIA, stop taking QSYMIA immediately and tell your health care provider right away. Health care providers and patients who become pregnant should report all cases of pregnancy to:
  - FDA MedWatch at 1-800-FDA-1088
  Because of the risk for birth defects (cleft lip and cleft palate), QSYMIA is available through a restricted program called the QSYMIA Risk Evaluation and Mitigation Strategy (REMS). QSYMIA is only available through certified pharmacies that participate in the QSYMIA REMS program. Your health care provider can give you information about how to find a certified pharmacy. For more information, go to www.QSYMIAREMS.com or call 1-888-998-4887.
- Suicidal thoughts or actions. Topiramate, an ingredient in QSYMIA, may cause you to have suicidal thoughts or actions.
  Call your health care provider right away if you have any of these symptoms, especially if they are new, worse, or worry you:
  - thoughts about suicide or dying
  - attempts to commit suicide
  - new or worse depression
  - new or worse anxiety
  - feeling agitated or restless
  - panic attacks
  - trouble sleeping (insomnia)
  - new or worse irritability
  - acting aggressive, being angry, or violent
  - acting on dangerous impulses
  - an extreme increase in activity and talking (mania)
  - other unusual changes in behavior or mood
  Do not stop QYSMIA without first talking to a health care provider.
  - Stopping QYSMIA suddenly can cause serious problems.
  - Suicidal thoughts or actions can be caused by things other than medicines. If you have suicidal thoughts or actions, your health care provider may check for other causes.
  How can I watch for early symptoms of suicidal thoughts and actions?
  - Pay attention to any changes, especially sudden changes in mood, behaviors, thoughts, or feelings.
  - Keep all follow-up visits with your health care provider as scheduled.
  - Call your health care provider between visits as needed, especially if you are worried about symptoms.
- Serious eye problems which include:
  - any sudden decrease in vision, with or without eye pain and redness,
  - a blockage of fluid in the eye causing increased pressure in the eye (secondary angle closure glaucoma).
  These problems can lead to permanent vision loss if not treated. Tell your health care provider right away if you have any new eye symptoms.

QSYMIA can have other serious side effects. See " What are the possible side effects of QSYMIA?"

What is QSYMIA?

- QSYMIA is a prescription medicine that contains phentermine and topiramate extended-release. QSYMIA may help adults and children 12 years and older with obesity, or some adults with overweight who also have weight-related medical problems, to help them lose excess body weight and keep the weight off.
- QSYMIA should be used with a reduced calorie diet and increased physical activity.
- It is not known if QSYMIA changes your risk of heart problems or stroke or of death due to heart problems or stroke.
- It is not known if QSYMIA is safe and effective when taken with other prescription and over-the-counter medicines, or herbal weight loss products.
- It is not known if QSYMIA is safe and effective in children under 12 years old.
- QSYMIA is a federally controlled substance (CIV) because it contains phentermine and can be abused or lead to drug dependence. Keep QSYMIA in a safe place, to protect it from theft. Never give your QSYMIA to anyone else, because it may cause death or harm them. Selling or giving away QSYMIA is against the law.

Who should not take QSYMIA? Do not take QSYMIA if you:

- are pregnant, planning to become pregnant, or become pregnant during QSYMIA treatment.
- have glaucoma.
- have thyroid problems (hyperthyroidism).
- are taking certain medicines called monoamine oxidase inhibitors (MAOIs) or have taken MAOIs in the past 14 days.
- are allergic to topiramate, sympathomimetic amines such as phentermine, or any of the ingredients in QSYMIA.
  See the end of this Medication Guide for a complete list of ingredients in QSYMIA.

Before taking QSYMIA, tell your health care provider about all of your medical conditions, including if you:

- have or have had depression, mood problems, or suicidal thoughts or behavior.
- have eye problems, especially glaucoma. See " Who should not take QSYMIA?"
- have a history of too much acid in the blood (metabolic acidosis) or a condition that puts you at higher risk for metabolic acidosis such as
  - chronic diarrhea, surgery, a diet high in fat and low in carbohydrates (ketogenic diet), weak, brittle, or soft bones (osteoporosis, osteomalacia (rickets), osteopenia), or decreased bone density.
- have kidney problems, kidney stones, or are getting kidney dialysis.
- have liver problems.
- have seizures or convulsions (epilepsy).
- are breastfeeding or plan to breastfeed. QSYMIA can pass into your breast milk and may harm your baby. You and your health care provider should decide if you will take QSYMIA or breastfeed. You should not do both.

Tell your health care provider about all the medicines you take, including prescription and over-the-counter medicines, vitamins, and herbal supplements. QSYMIA taken with other medicines may affect how each medicine works and may cause side effects.
Especially tell your health care provider if you take:

- Birth control pills. Tell your health care provider if your menstrual bleeding changes while you are taking birth control pills that contain both estrogen and progestin (combination oral contraceptives) and QSYMIA.
- Water pills (diuretics) such as hydrochlorothiazide (HCTZ).
- Any medicines that impair or decrease your thinking, concentration, or muscle coordination.
- Carbonic anhydrase inhibitors such as ZONEGRAN (zonisamide), DIAMOX (acetazolamide) or NEPTAZANE (methazolamide).
- Seizure medicines such as Valproic acid (DEPAKENE or DEPAKOTE).

Ask your health care provider or pharmacist for a list of these medicines, if you are not sure.
Know the medicines you take. Keep a list of them to show your health care provider and pharmacist each time you get a new medicine. Do not start a new medicine without talking to your health care provider.

How should I take QSYMIA?

- Your health care provider should start you on a diet and exercise program when you start taking QSYMIA. Stay on this program while you are taking QSYMIA.
- Take QSYMIA exactly as your health care provider tells you to take it.
- Do not change your dose without talking to your health care provider.
- Take QSYMIA daily in the morning.
- QSYMIA can be taken with or without food.
- If you miss a dose of QSYMIA, wait until the next morning to take your usual dose of QSYMIA. Do not double your dose.
- To start treatment with QSYMIA
  - Take 1 QSYMIA 3.75 mg (phentermine)/23 mg (topiramate) capsule (Figure A) 1 time each morning for the first 14 days.
  - After taking QSYMIA 3.75 mg/23 mg capsule for 14 days, then take 1 QSYMIA 7.5 mg/46 mg capsule (Figure B) 1 time each morning.
- After taking QSYMIA for 12 weeks
  - Your health care provider may tell you to increase your dose of QSYMIA if you do not lose a certain amount of weight or do not have a certain decrease in BMI for children 12 years and older, within the first 12 weeks of treatment at the recommended dose.
- If your health care provider increases the dose of QSYMIA
  - Take 1 QSYMIA 11.25 mg/69 mg capsule (Figure C) 1 time each morning for 14 days.
  - After taking 14 days of QSYMIA 11.25 mg/69 mg capsule, then take 1 QSYMIA 15 mg/92 mg capsule (Figure D) 1 time each morning.
- Stopping QSYMIA treatment
  Your health care provider should tell you to stop taking QSYMIA if you have not lost a certain amount of weight or do not have a certain decrease in BMI for children 12 years and older, after an additional 12 weeks of treatment on the higher dose.
  Do notstop taking QSYMIA without talking to your health care provider. Stopping QSYMIA suddenly can cause serious problems, such as seizures. Your health care provider will tell you how to stop taking QSYMIA slowly.

If you take too much QSYMIA, call your health care provider or Poison Help line at 1-800-222-1222 or go to the nearest emergency room right away.

What should I avoid while taking QSYMIA?

- Do not get pregnant while taking QSYMIA. See " What is the most important information I should know about QSYMIA".
- Do not drink too much alcohol while taking QSYMIA. QSYMIA and alcohol can affect each other causing side effects such as sleepiness or dizziness.
- Do not drive a car, operate heavy machinery, or do other dangerous activities until you know how QSYMIA affects you.QSYMIA can slow your thinking and motor skills and may affect vision.

What are the possible side effects of QSYMIA?
QSYMIA can cause serious side effects, including:

- See " What is the most important information I should know about QSYMIA?"
- Mood changes and trouble sleeping. QSYMIA may cause depression or mood problems, and trouble sleeping. Tell your health care provider if symptoms occur.
- Concentration, memory, and speech difficulties. QSYMIA may affect how you think and cause confusion, problems with concentration, attention, memory, or speech. Tell your health care provider if symptoms occur.
- Slowing of growth. QSYMIA may slow the increase in height in children 12 years and older, when used for a long time.
- Increases of acid in bloodstream (metabolic acidosis). If left untreated, metabolic acidosis can cause brittle or soft bones (osteoporosis, osteomalacia (rickets), osteopenia), kidney stones, can slow the rate of growth in children, and may possibly harm your baby if you are pregnant. Metabolic acidosis can happen with or without symptoms. Sometimes people with metabolic acidosis will:
  - feel tired
  - not feel hungry (loss of appetite)
  - feel changes in heartbeat
  - have trouble thinking clearly
  Your health care provider should do a blood test to measure the level of acid in your blood before and during your treatment with QSYMIA.
- Decrease in kidney function. QSYMIA may cause a decrease in kidney function. Your health care provider should do a blood test to measure your kidney function before and during treatment with QSYMIA.
- Possible seizures if you stop taking QSYMIA too fast. Seizures may happen in people who may or may not have had seizures in the past if you stop QSYMIA too fast. Your health care provider will tell you how to stop taking QSYMIA slowly.
- Kidney stones. Drink plenty of fluids when taking QSYMIA to help decrease your chances of getting kidney stones. If you get severe side or back pain, or blood in your urine, call your health care provider.
- Decreased sweating and increased body temperature (fever). People should be watched for signs of decreased sweating and fever, especially in hot temperatures. Some people may need to be hospitalized for this condition.
- Low potassium. QSYMIA can increase your risk of low potassium levels. Your health care provider should do a blood test to measure the level of potassium in your blood before and during treatment with QSYMIA.
- Serious skin reactions. QSYMIA may cause a severe rash with blisters and peeling skin, especially around the mouth, nose, eyes, and genitals (Stevens-Johnson Syndrome). QSYMIA may also cause a rash with blisters and peeling skin over much of the body that may cause death (Toxic Epidermal Necrolysis). Call your health care provider right away if you develop a skin rash or blisters.
- Allergic reaction to FD&C Yellow No. 5. QSYMIA capsules contain the inactive ingredient FD&C Yellow No. 5 (tartrazine) which can cause allergic-type reactions (including bronchial asthma) in certain people, especially people who also have an allergy to aspirin.

Common side effects of QSYMIA in adults include:

- numbness or tingling in the hands, arms, feet, or face (paraesthesia)
- dizziness
- change in the way foods taste or loss of taste (dysgeusia)
- trouble sleeping (insomnia)
- constipation
- dry mouth

Common side effects of QSYMIA in children 12 years and older include:

- depression
- dizziness
- joint pain
- fever
- flu
- ankle sprain

Tell your health care provider if you have any side effect that bothers you or does not go away.
These are not all of the possible side effects of QSYMIA. For more information, ask your health care provider or pharmacist.
Call your doctor for medical advice about side effects. You may report side effects to FDA at 1-800-FDA-1088.
You can also report side effects to VIVUS at 1-888-998-4887.

How should I store QSYMIA?

- Store QSYMIA at room temperature between 68°F to 77°F (20°C to 25°C).
- Keep QSYMIA in a tightly closed container.
- Keep QSYMIA dry and away from moisture.

Keep QSYMIA and all medicines out of the reach of children.

General Information about the safe and effective use of QSYMIA.
Medicines are sometimes prescribed for purposes other than those listed in a Medication Guide. Do not use QSYMIA for a condition for which it was not prescribed. Do not give QSYMIA to other people, even if they have the same symptoms you have. It may harm them.
You can ask your pharmacist or health care provider for information about QSYMIA that is written for health professionals.

What are the ingredients in QSYMIA?
Active Ingredient: phentermine hydrochloride and topiramate extended-release.
Inactive Ingredients: FD&C Blue #1, FD&C Red #3, FD&C Yellow #5 and #6, ethylcellulose, gelatin, methylcellulose,
microcrystalline cellulose, povidone, starch, sucrose, talc, titanium dioxide, and pharmaceutical black and white inks.
Copyright © 2012 - 2025 VIVUS LLC All rights reserved.
VIVUS LLC
900 E. Hamilton Ave., Suite 550
Campbell, CA 95008 USA
US Patent Numbers: 7,056,890; 7,553,818; 7,659,256; 7,674,776; 8,580,298; 8,580,299; 8,895,057; 8,895,058; 9,011,905; and 9,011,906.
QSYMIA is a registered trademark of VIVUS LLC.

This Medication Guide has been approved by the U.S. Food and Drug Administration.
PH-03-002-16

Revised: 09/2024

PRINCIPAL DISPLAY PANEL - 7.5 mg/46 mg Capsule Bottle Label

NDC NUMBER 62541-202-30

QSYMIA®
(phentermine and topiramate
extended-release capsules) CIV

7.5 mg/46 mg

30 Capsules

Rx only

DISPENSE WITH MEDICATION GUIDE

PRINCIPAL DISPLAY PANEL - 3.75 mg/23 mg Capsule Bottle Label

NDC NUMBER 62541-201-30

QSYMIA®
(phentermine and topiramate
extended-release capsules) CIV

3.75 mg/23 mg

30 Capsules

Rx only

DISPENSE WITH MEDICATION GUIDE

PRINCIPAL DISPLAY PANEL - 15 mg/92 mg Capsule Bottle Label

NDC NUMBER 62541-204-30

QSYMIA®
(phentermine and topiramate
extended-release capsules) CIV

15 mg/92 mg

30 Capsules

Rx only

DISPENSE WITH MEDICATION GUIDE

PRINCIPAL DISPLAY PANEL - 11.25 mg/69 mg Capsule Bottle Label

NDC NUMBER 62541-203-30

QSYMIA®
(phentermine and topiramate
extended-release capsules) CIV

11.25 mg/69 mg

30 Capsules

Rx only

DISPENSE WITH MEDICATION GUIDE